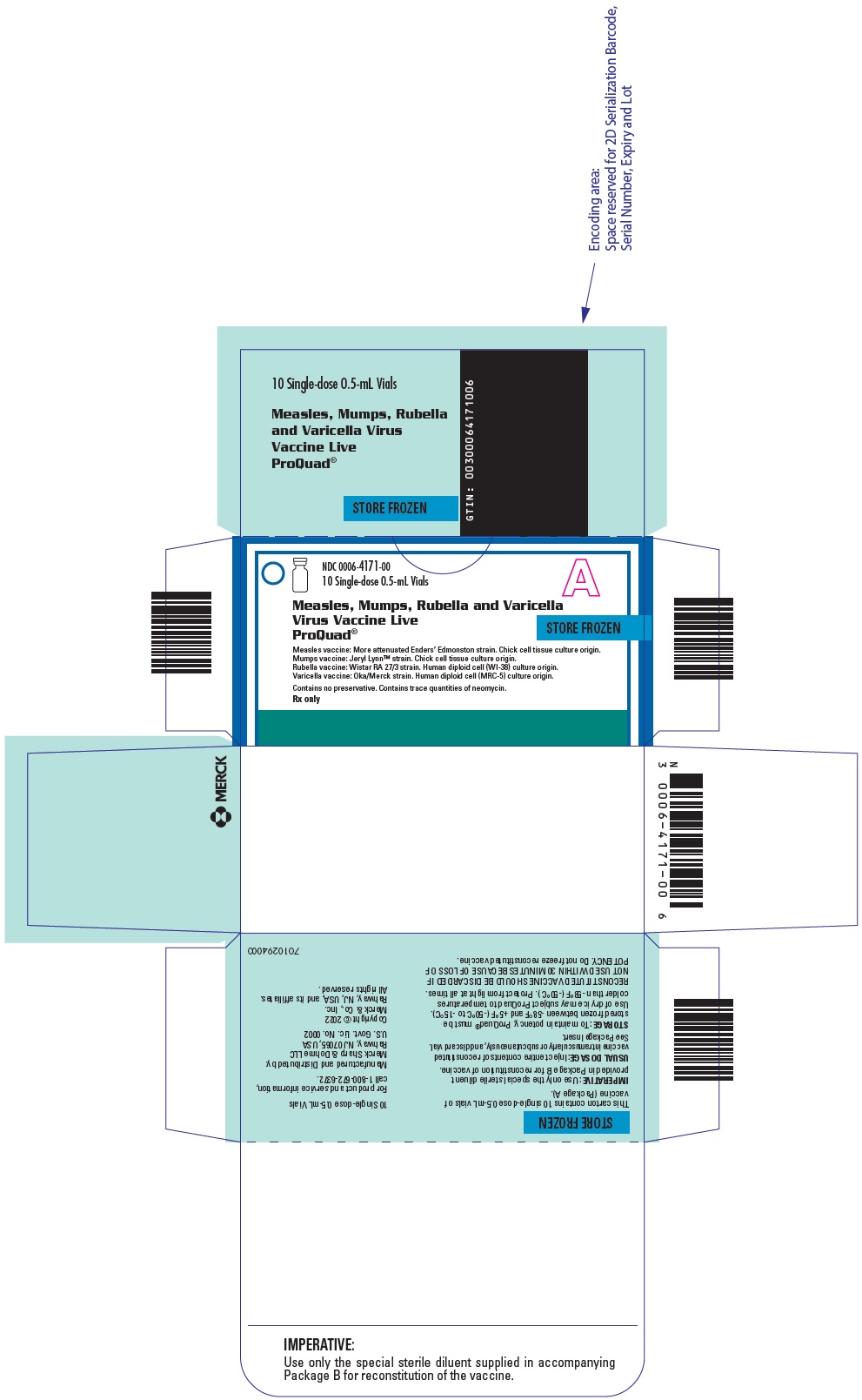 DRUG LABEL: ProQuad
NDC: 0006-4171 | Form: INJECTION, POWDER, LYOPHILIZED, FOR SUSPENSION
Manufacturer: Merck Sharp & Dohme LLC
Category: other | Type: VACCINE LABEL
Date: 20251107

ACTIVE INGREDIENTS: MEASLES VIRUS STRAIN ENDERS' ATTENUATED EDMONSTON LIVE ANTIGEN 1000 [TCID_50]/0.5 mL; MUMPS VIRUS STRAIN B LEVEL JERYL LYNN LIVE ANTIGEN 20000 [TCID_50]/0.5 mL; RUBELLA VIRUS STRAIN WISTAR RA 27/3 LIVE ANTIGEN 1000 [TCID_50]/0.5 mL; VARICELLA-ZOSTER VIRUS STRAIN OKA/MERCK LIVE ANTIGEN 9772 [PFU]/0.5 mL
INACTIVE INGREDIENTS: ALBUMIN HUMAN 0.31 mg/0.5 mL; ALBUMIN BOVINE 0.5 ug/0.5 mL; GELATIN, UNSPECIFIED 11 mg/0.5 mL; MONOSODIUM GLUTAMATE 0.4 mg/0.5 mL; NEOMYCIN 16 ug/0.5 mL; POTASSIUM CHLORIDE 60 ug/0.5 mL; DIBASIC POTASSIUM PHOSPHATE 36 ug/0.5 mL; POTASSIUM PHOSPHATE, MONOBASIC 72 ug/0.5 mL; SODIUM BICARBONATE 0.17 mg/0.5 mL; SODIUM CHLORIDE 2.4 mg/0.5 mL; SODIUM PHOSPHATE, DIBASIC, UNSPECIFIED FORM 0.34 mg/0.5 mL; SORBITOL 1.8 mg/0.5 mL; SUCROSE 21 mg/0.5 mL

HIGHLIGHTS OF PRESCRIBING INFORMATION

These highlights do not include all the information needed to use ProQuad safely and effectively. See full prescribing information for ProQuad.
ProQuad® (Measles, Mumps, Rubella and Varicella Virus Vaccine Live) for injectable suspension, for intramuscular or subcutaneous use
Initial U.S. Approval: 2005

1 INDICATIONS AND USAGE

ProQuad is a vaccine indicated for active immunization for the prevention of measles, mumps, rubella, and varicella in children 12 months through 12 years of age. (1)

2 DOSAGE AND ADMINISTRATION

For intramuscular or subcutaneous use. (2.1, 2.3)
A single dose is approximately 0.5 mL.

- The first dose is administered at 12 to 15 months of age. (2.1)
- The second dose is administered at 4 to 6 years of age. (2.1)

3 DOSAGE FORMS AND STRENGTHS

For injectable suspension. ProQuad (approximately 0.5 mL dose) is supplied as a lyophilized vaccine to be reconstituted using accompanying sterile diluent. (2.2, 3)

4 CONTRAINDICATIONS

- Hypersensitivity to any component of the vaccine. (4.1)
- Immunosuppression. (4.2)
- Moderate or severe febrile illness. (4.3)
- Active untreated tuberculosis. (4.4)
- Pregnancy. (4.5, 8.1)

5 WARNINGS AND PRECAUTIONS

- Administration of ProQuad (dose 1) to children 12 to 23 months old who have not been previously vaccinated against measles, mumps, rubella, or varicella, nor had a history of the wild-type infections, is associated with higher rates of fever and febrile seizures at 5 to 12 days after vaccination when compared to children vaccinated with M-M-R® II and VARIVAX® administered separately. Exercise caution when administering ProQuad to persons with an individual or family history of febrile seizures. (5.1, 6.1, 6.3)
- Use caution when administering ProQuad to children with anaphylaxis or immediate hypersensitivity following egg ingestion. (5.2)
- Use caution when administering ProQuad to children with thrombocytopenia. (5.3)
- Evaluate individuals for immune competence prior to administration of ProQuad if there is a family history of congenital or hereditary immunodeficiency. (5.4)
- Avoid close contact with high-risk individuals susceptible to varicella because of possible transmission of varicella vaccine virus. (5.6)
- Immune Globulins (IG) and other blood products should not be given concurrently with ProQuad. (5.7, 7.2)
- Avoid using salicylates for 6 weeks after vaccination with ProQuad. (5.8, 7.3, 17)

6 ADVERSE REACTIONS

- The most frequent vaccine-related adverse events reported in ≥5% of subjects vaccinated with ProQuad were:
  - injection-site reactions (pain/tenderness/soreness, erythema, and swelling)
  - fever
  - irritability. (6.1)
- Systemic vaccine-related adverse events that were reported at a significantly greater rate in recipients of ProQuad than in recipients of the component vaccines administered concomitantly were:
  - fever
  - measles-like rash. (6.1)

To report SUSPECTED ADVERSE REACTIONS, contact Merck Sharp & Dohme LLC at 1-877-888-4231 or VAERS at 1-800-822-7967 or www.vaers.hhs.gov .

7 DRUG INTERACTIONS

- Administration of immune globulins and other blood products concurrently with ProQuad vaccine may interfere with the expected immune response. (7.2)
- ProQuad vaccination may result in a temporary depression of purified protein derivative (PPD) tuberculin skin sensitivity. (7.4)
- ProQuad may be administered concomitantly with Haemophilus influenzae type b conjugate vaccine and/or hepatitis B vaccine at separate injection sites. (7.5)
- ProQuad may be administered concomitantly with pneumococcal 7-valent conjugate vaccine and/or hepatitis A vaccine (inactivated) at separate injection sites. (7.5)

8 USE IN SPECIFIC POPULATIONS

Pregnancy: Do not administer ProQuad to females who are pregnant. Pregnancy should be avoided for 3 months following vaccination with ProQuad. (4.5, 8.1, 17)

FULL PRESCRIBING INFORMATION

1 INDICATIONS AND USAGE

ProQuad is a vaccine indicated for active immunization for the prevention of measles, mumps, rubella, and varicella in children 12 months through 12 years of age.

2 DOSAGE AND ADMINISTRATION

For Intramuscular or Subcutaneous administration only

2.1 Dose and Schedule

A single dose of ProQuad is approximately 0.5 mL.

The first dose is administered at 12 to 15 months of age but may be given anytime through 12 years of age.

The second dose is administered at 4 to 6 years of age.

At least 1 month should elapse between a dose of a measles-containing vaccine and a dose of ProQuad. At least 3 months should elapse between a dose of varicella-containing vaccine and ProQuad.

2.2 Preparation for Administration

The sterile diluent for ProQuad is provided in either a vial or prefilled syringe.

Sterile Diluent Vial

Use a sterile syringe free of preservatives, antiseptics, and detergents for each injection and/or reconstitution of the vaccine because these substances may inactivate the live virus vaccine. To reconstitute, use the sterile diluent vial supplied with ProQuad. The sterile diluent does not contain preservatives or other antiviral substances which might inactivate the vaccine viruses.

To reconstitute the vaccine, withdraw the entire volume of the supplied sterile diluent from the vial and slowly inject into the lyophilized vaccine vial. Gently agitate to dissolve completely. Discard if the lyophilized vaccine cannot be dissolved.

Parenteral drug products should be inspected visually for particulate matter and discoloration prior to administration, whenever solution and container permit. Visually inspect the vaccine before and after reconstitution prior to administration. Before reconstitution, the lyophilized vaccine is a white to pale yellow compact crystalline plug. ProQuad, when reconstituted, is a clear pale yellow to light pink liquid. Do not use the reconstituted vaccine if particulates are present or if it appears discolored.

Withdraw and administer the entire volume of the reconstituted vaccine.

Administer ProQuad immediately after reconstitution. If not used immediately, the reconstituted vaccine may be stored at room temperature, protected from light, for up to 30 minutes. Discard reconstituted vaccine if it is not used within 30 minutes.

Sterile Diluent Prefilled Syringe

To reconstitute, use the sterile diluent prefilled syringe supplied with the vaccine since it does not contain preservatives or other antiviral substances which might inactivate the vaccine viruses.

Attach a needle to the prefilled syringe.

Reconstitute the vaccine by slowly injecting the entire volume of sterile diluent contained in the prefilled syringe into the lyophilized vaccine vial. Gently agitate to dissolve completely. Discard if the lyophilized vaccine cannot be dissolved.

Parenteral drug products should be inspected visually for particulate matter and discoloration prior to administration, whenever solution and container permit. Visually inspect the vaccine before and after reconstitution prior to administration. Before reconstitution, the lyophilized vaccine is a white to pale yellow compact crystalline plug. ProQuad, when reconstituted, is a clear pale yellow to light pink liquid. Do not use the reconstituted vaccine if particulates are present or if it appears discolored.

Withdraw and administer the entire volume of the reconstituted vaccine.

Administer ProQuad immediately after reconstitution. If not used immediately, the reconstituted vaccine may be stored at room temperature, protected from light, for up to 30 minutes. Discard reconstituted vaccine if it is not used within 30 minutes.

2.3 Administration

Inject the vaccine intramuscularly or subcutaneously.

3 DOSAGE FORMS AND STRENGTHS

For injectable suspension. ProQuad is supplied as a single dose vial of lyophilized vaccine to be reconstituted using the accompanying sterile diluent [see Dosage and Administration (2.2) and How Supplied/Storage and Handling (16)]. A single dose after reconstitution is approximately 0.5 mL.

4 CONTRAINDICATIONS

4.1 Hypersensitivity

Do not administer ProQuad to individuals with a history of hypersensitivity to any component of the vaccine (including gelatin) {1} or to a previous dose of M-M-R II (Measles, Mumps, Rubella, Live), ProQuad or VARIVAX (Varicella Virus Vaccine Live) vaccine, or any other measles, mumps, and rubella or varicella-containing vaccine. Do not administer ProQuad to individuals with a history of anaphylaxis to neomycin [see Description (11)].

4.2 Immunosuppression

Do not administer ProQuad vaccine to individuals who are immunodeficient or immunosuppressed due to disease or medical therapy. Measles inclusion body encephalitis {2} (MIBE), pneumonitis {3} and death as a direct consequence of disseminated measles vaccine virus infection have been reported in immunocompromised individuals inadvertently vaccinated with measles-containing vaccine. In this population, disseminated mumps and rubella vaccine virus infection have also been reported. Disseminated varicella disease and extensive vaccine-associated rash have been reported in individuals who are immunosuppressed or immunodeficient who were inadvertently vaccinated with a varicella-containing vaccine {4}.

4.3 Moderate or Severe Febrile Illness

Do not administer ProQuad to individuals with an active febrile illness with fever >101.3°F (>38.5°C).

4.4 Active Untreated Tuberculosis

Do not administer ProQuad vaccine to individuals with active untreated tuberculosis (TB).

4.5 Pregnancy

Do not administer ProQuad to individuals who are pregnant or planning on becoming pregnant in the next 3 months [see Use in Specific Populations (8.1) and Patient Counseling Information (17)].

5 WARNINGS AND PRECAUTIONS

5.1 Fever and Febrile Seizures

Administration of ProQuad (dose 1) to children 12 to 23 months old who have not been previously vaccinated against measles, mumps, rubella, or varicella, nor had a history of the wild-type infections, is associated with higher rates of fever and febrile seizures at 5 to 12 days after vaccination when compared to children vaccinated with a first dose of M-M-R II and VARIVAX administered concomitantly [see Adverse Reactions (6.3)]. Exercise caution when administering ProQuad to persons with an individual or family history of febrile seizures.

5.2 Hypersensitivity to Eggs

Individuals with a history of anaphylactic, anaphylactoid, or other immediate reactions (e.g., hives, swelling of the mouth and throat, difficulty breathing, hypotension, or shock) subsequent to egg ingestion may be at an enhanced risk of immediate-type hypersensitivity reactions after receiving ProQuad vaccine. The potential risks and known benefits should be evaluated before considering vaccination in these individuals [see Contraindications (4.1)] {5}.

5.3 Thrombocytopenia

Transient thrombocytopenia has been reported within 4-6 weeks following vaccination with measles, mumps and rubella vaccine. Carefully evaluate the potential risk and benefit of vaccination in children with thrombocytopenia or in those who experienced thrombocytopenia after vaccination with a previous dose of a measles, mumps, and rubella-containing vaccine [see Adverse Reactions (6.2)] {6-8}.

5.4 Family History of Immunodeficiency

Vaccination should be deferred in individuals with a family history of congenital or hereditary immunodeficiency until the individual's immune status has been evaluated and the individual has been found to be immunocompetent.

5.5 Use in HIV-Infected Individuals

The Advisory Committee on Immunization Practices (ACIP) has recommendations on the use of varicella vaccine in HIV-infected individuals.

5.6 Risk of Vaccine Virus Transmission

Post-licensing experience suggests that transmission of varicella vaccine virus (Oka/Merck) resulting in varicella infection including disseminated disease may occur between vaccine recipients (who develop or do not develop a varicella-like rash) and contacts susceptible to varicella including healthy as well as high-risk individuals.

High-risk individuals susceptible to varicella include:

- Immunocompromised individuals;
- Pregnant women without documented positive history of varicella (chickenpox) or laboratory evidence of prior infection;
- Newborn infants of mothers without documented positive history of varicella or laboratory evidence of prior infection and all newborn infants born at <28 weeks gestation regardless of maternal varicella immunity.

Vaccine recipients should attempt to avoid, to the extent possible, close association with high-risk individuals susceptible to varicella for up to 6 weeks following vaccination. In circumstances where contact with high-risk individuals susceptible to varicella is unavoidable, the potential risk of transmission of the varicella vaccine virus should be weighed against the risk of acquiring and transmitting wild-type varicella virus.

Excretion of small amounts of the live, attenuated rubella virus from the nose or throat has occurred in the majority of susceptible individuals 7 to 28 days after vaccination. There is no confirmed evidence to indicate that such virus is transmitted to susceptible persons who are in contact with the vaccinated individuals. Consequently, transmission through close personal contact, while accepted as a theoretical possibility, is not regarded as a significant risk. However, transmission of the rubella vaccine virus to infants via breast milk has been documented [see Use in Specific Populations (8.2)].

There are no reports of transmission of the more attenuated Enders' Edmonston strain of measles virus or the Jeryl Lynn™ strain of mumps virus from vaccine recipients to susceptible contacts.

5.7 Immune Globulins and Other Blood Products

Immune Globulins (IG) and other blood products should not be given concurrently with ProQuad [see Drug Interactions (7.2)]. These products may contain antibodies that interfere with vaccine virus replication and decrease the expected immune response.

The U.S. Centers for Disease Control and Prevention (CDC) has specific recommendations for intervals between administration of antibody containing products and live virus vaccines.

5.8 Salicylate Therapy

Avoid the use of salicylates (aspirin) or salicylate-containing products in children and adolescents 12 months through 12 years of age, for six weeks following vaccination with ProQuad due to the association of Reye syndrome with salicylate therapy and wild-type varicella infection [see Drug Interactions (7.3) and Patient Counseling Information (17)].

6 ADVERSE REACTIONS

6.1 Clinical Trials Experience

Because clinical trials are conducted under widely varying conditions, adverse reaction rates observed in the clinical trials of a vaccine cannot be directly compared to rates in the clinical trials of another vaccine and may not reflect the rates observed in practice. Vaccine-related adverse reactions reported during clinical trials were assessed by the study investigators to be possibly, probably, or definitely vaccine-related and are summarized below.

Children 12 Through 23 Months of Age Who Received a Single Dose of ProQuad

ProQuad was administered subcutaneously to 4497 children 12 through 23 months of age involved in 4 randomized clinical trials without concomitant administration with other vaccines. The safety of ProQuad was compared with the safety of M-M-R II and VARIVAX given concomitantly (N=2038) at separate injection sites. The safety profile for ProQuad was similar to the component vaccines. Children in these studies were monitored for up to 42 days postvaccination using vaccination report card-aided surveillance. Safety follow-up was obtained for 98% of children in each group. Few subjects (<0.1%) who received ProQuad discontinued the study due to an adverse reaction. The race distribution of the study subjects across these studies following a first dose of ProQuad was as follows: 65.2% White; 13.1% African-American; 11.1% Hispanic; 5.8% Asian/Pacific; 4.5% other; and 0.2% American Indian. The racial distribution of the control group was similar to that of the group who received ProQuad. The gender distribution across the studies following a first dose of ProQuad was 52.5% male and 47.5% female. The gender distribution of the control group was similar to that of the group who received ProQuad. Vaccine-related injection-site and systemic adverse reactions observed among recipients of ProQuad or M-M-R II and VARIVAX at a rate of at least 1% are shown in Table 1. Systemic vaccine-related adverse reactions that were reported at a significantly greater rate in individuals who received a first dose of ProQuad than in individuals who received first doses of M-M-R II and VARIVAX concomitantly at separate injection sites were fever (≥102°F [≥38.9°C] oral equivalent or abnormal) (21.5% versus 14.9%, respectively, risk difference 6.6%, 95% CI: 4.6, 8.5), and measles-like rash (3.0% versus 2.1%, respectively, risk difference 1.0%, 95% CI: 0.1, 1.8). Both fever and measles-like rash usually occurred within 5 to 12 days following the vaccination, were of short duration, and resolved with no long-term sequelae. Pain/tenderness/soreness at the injection site was reported at a statistically lower rate in individuals who received ProQuad than in individuals who received M-M-R II and VARIVAX concomitantly at separate injection sites (22.0% versus 26.8%, respectively, risk difference -4.8%, 95% CI: -7.1, -2.5). The only vaccine-related injection-site adverse reaction that was more frequent among recipients of ProQuad than recipients of M-M-R II and VARIVAX was rash at the injection site (2.4% versus 1.6%, respectively, risk difference 0.9%, 95% CI: 0.1, 1.5).

Table 1: Vaccine-Related Injection-Site and Systemic Adverse Reactions Reported in ≥1% of Children Who Received ProQuad Dose 1 or M-M-R II and VARIVAX at 12 to 23 Months of Age (0 to 42 Days Postvaccination)
 | ProQuad (N=4497) | M-M-R II and VARIVAX (N=2038)
Adverse Reactions | (n=4424) % | (n=1997) %
Injection Site [Injection-site adverse reactions for M-M-R II and VARIVAX are based on occurrence with either of the vaccines administered.]
Pain/tenderness/soreness [Designates a solicited adverse reaction. Injection-site adverse reactions were solicited only from Days 0 to 4 postvaccination.] | 22.0 | 26.7
Erythema | 14.4 | 15.8
Swelling | 8.4 | 9.8
Ecchymosis | 1.5 | 2.3
Rash | 2.3 | 1.5
Systemic
Fever, [Temperature reported as elevated (≥102°F, oral equivalent) or abnormal.] | 21.5 | 14.9
Irritability | 6.7 | 6.7
Measles-like rash | 3.0 | 2.1
Varicella-like rash | 2.1 | 2.2
Rash (not otherwise specified) | 1.6 | 1.4
Upper respiratory infection | 1.3 | 1.1
Viral exanthema | 1.2 | 1.1
Diarrhea | 1.2 | 1.3
N = number of subjects vaccinated.
n = number of subjects with safety follow-up.

Rubella-like rashes were observed in <1% of subjects following a first dose of ProQuad.

In these clinical trials, two cases of herpes zoster were reported among 2108 healthy subjects 12 through 23 months of age who were vaccinated with their first dose of ProQuad and followed for 1 year. Both cases were unremarkable and no sequelae were reported.

Children 15 to 31 Months of Age Who Received a Second Dose of ProQuad

In 5 clinical trials, 2780 healthy children were vaccinated subcutaneously with ProQuad (dose 1) at 12 to 23 months of age and then administered a second dose approximately 3 to 9 months later. The race distribution of the study subjects across these studies following a second dose of ProQuad was as follows: 64.4% White; 14.1% African-American; 12.0% Hispanic; 5.9% other; 3.5% Asian/Pacific; and 0.1% American Indian. The gender distribution across the studies following a second dose of ProQuad was 51.5% male and 48.5% female. Children in these open-label studies were monitored for at least 28 days postvaccination using vaccination report card-aided surveillance. Safety follow-up was obtained for approximately 97% of children overall. Vaccine-related injection-site and systemic adverse reactions observed after Dose 1 and 2 of ProQuad at a rate of at least 1% are shown in Table 2. In these trials, the overall rates of systemic adverse reactions after ProQuad (dose 2) were comparable to, or lower than, those seen with the first dose. In the subset of children who received both ProQuad dose 1 and dose 2 in these trials (N=2408) with follow-up for fever, fever ≥102.2°F (≥38.9°C) was observed significantly less frequently days 1 to 28 after the second dose (10.8%) than after the first dose (19.1%) (risk difference 8.3%, 95% CI: 6.4, 10.3). Fevers ≥102.2°F (≥38.9°C) days 5 to 12 after vaccinations were also reported significantly less frequently after dose 2 (3.9%) than after dose 1 (13.6%) (risk difference 9.7%, 95% CI: 8.1, 11.3). In the subset of children who received both doses and for whom injection-site reactions were reported (N=2679), injection-site erythema was noted significantly more frequently after ProQuad (dose 2) as compared to ProQuad (dose 1) (12.6% and 10.8%, respectively, risk difference -1.8, 95% CI: -3.3, -0.3); however, pain and tenderness at the injection site was significantly lower after dose 2 (16.1%) as compared with after dose 1 (21.9%) (risk difference, 5.8%, 95% CI: 4.1, 7.6). Two children had febrile seizures after ProQuad (dose 2); both febrile seizures were thought to be related to a concurrent viral illness [see Adverse Reactions (6.3) and Clinical Studies (14)]. These studies were not designed or statistically powered to detect a difference in rates of febrile seizure between recipients of ProQuad as compared to M-M-R II and VARIVAX. The risk of febrile seizure has not been evaluated in a clinical study comparing the incidence rate after ProQuad (dose 2) with the incidence rate after concomitant M-M-R II (dose 2) and VARIVAX (dose 2) [see Adverse Reactions (6.1), Children 4 to 6 Years of Age Who Received ProQuad After Primary Vaccination with M-M-R II and VARIVAX].

Table 2: Vaccine-Related Injection-Site and Systemic Adverse Reactions Reported in ≥1% of Children Who Received ProQuad Dose 1 at 12 to 23 Months of Age and Dose 2 at 15 to 31 Months of Age (1 to 28 Days Postvaccination)
 | ProQuad Dose 1 | ProQuad Dose 2
Adverse Reactions | (N=3112) (n=3019) % | (N=2780) (n=2695) %
Injection-Site
Pain/tenderness/soreness [Designates a solicited adverse reaction. Injection-site adverse reactions were solicited only from Days 1 to 5 postvaccination.] | 21.4 | 15.9
Erythema | 10.7 | 12.4
Swelling | 8.0 | 8.5
Injection-site bruising | 1.1 | 0.0
Systemic
Fever, [Temperature reported as elevated or abnormal.] | 20.4 | 8.3
Irritability | 6.0 | 2.4
Measles-like/Rubella-like rash | 4.3 | 0.9
Varicella-like/Vesicular rash | 1.5 | 0.1
Diarrhea | 1.3 | 0.6
Upper respiratory infection | 1.3 | 1.4
Rash (not otherwise specified) | 1.2 | 0.6
Rhinorrhea | 1.1 | 1.0
N = number of subjects vaccinated.
n = number of subjects with safety follow-up.

Children 4 to 6 Years of Age Who Received ProQuad After Primary Vaccination with M-M-R II and VARIVAX

In a double-blind clinical trial, 799 healthy 4- to 6-year-old children who received M-M-R II and VARIVAX at least 1 month prior to study entry were randomized to receive ProQuad administered subcutaneously and placebo (N=399), M-M-R II and placebo concomitantly (N=205) at separate injection sites, or M-M-R II and VARIVAX (N=195) concomitantly at separate injection sites [see Clinical Studies (14)]. Children in these studies were monitored for up to 42 days postvaccination using vaccination report card-aided surveillance. Safety follow-up was obtained for >98% of children in each group. The race distribution of the study subjects following a dose of ProQuad was as follows: 78.4% White; 12.3% African-American; 3.8% Hispanic; 3.5% other; and 2.0% Asian/Pacific. The gender distribution following a dose of ProQuad was 52.1% male and 47.9% female. Injection-site and systemic adverse reactions observed after Dose 1 and 2 of ProQuad at a rate of at least 1% are shown in Table 3 [see Clinical Studies (14)].

Table 3: Vaccine-Related Injection-Site and Systemic Adverse Reactions Reported in ≥1% of Children Previously Vaccinated with M-M-R II and VARIVAX Who Received ProQuad + Placebo, M-M-R II + Placebo, or M-M-R II + VARIVAX at 4 to 6 Years of Age (1 to 43 Days Postvaccination)
Adverse Reactions | ProQuad + Placebo (N=399) (n=397) % |  | M-M-R II + Placebo (N=205) (n=205) % |  | M-M-R II + VARIVAX (N=195) (n=193) %
Systemic
Fever [Designates a solicited adverse reaction. Injection-site adverse reactions were solicited only from Days 1 to 5 postvaccination.] , [Temperature reported as elevated (≥102°F, oral equivalent) or abnormal.] | 2.5 |  | 2.0 |  | 4.1
Cough | 1.3 |  | 0.5 |  | 0.5
Irritability | 1.0 |  | 0.5 |  | 1.0
Headache | 0.8 |  | 1.5 |  | 1.6
Rhinorrhea | 0.5 |  | 1.0 |  | 0.5
Nasopharyngitis | 0.3 |  | 1.0 |  | 1.0
Vomiting | 0.3 |  | 1.0 |  | 0.5
Upper respiratory infection | 0.0 |  | 0.0 |  | 1.0
 | ProQuad % | Placebo % | M-M-R II % | Placebo % | M-M-R II % | VARIVAX %
Injection-Site
Pain | 41.1 | 34.5 | 36.6 | 34.1 | 35.2 | 36.8
Erythema | 24.4 | 13.4 | 15.6 | 14.1 | 14.5 | 15.5
Swelling | 15.6 | 8.1 | 10.2 | 8.8 | 7.8 | 10.9
Bruising | 3.5 | 3.8 | 2.4 | 3.4 | 1.6 | 2.1
Rash | 1.5 | 1.3 | 0.0 | 0.0 | 0.5 | 0.0
Pruritus | 1.0 | 0.3 | 0.0 | 0.0 | 0.0 | 1.0
Nodule | 0.0 | 0.0 | 0.0 | 0.0 | 0.0 | 1.0
N = number of subjects vaccinated.
n = number of subjects with safety follow-up.

Safety in Trials That Evaluated Concomitant Use with Other Vaccines

ProQuad Administered with Diphtheria and Tetanus Toxoids and Acellular Pertussis Vaccine Adsorbed (DTaP) and Haemophilus influenzae type b Conjugate (Meningococcal Protein Conjugate) and Hepatitis B (Recombinant) Vaccine

In an open-label clinical trial, 1434 children were randomized to receive ProQuad administered subcutaneously given with diphtheria and tetanus toxoids and acellular pertussis vaccine adsorbed (DTaP) and Haemophilus influenzae type b conjugate (meningococcal protein conjugate) and hepatitis B (recombinant) vaccine concomitantly (N=949) or non-concomitantly with ProQuad given first and the other vaccines 6 weeks later (N=485). No clinically significant differences in adverse events were reported between treatment groups [see Clinical Studies (14)]. The race distribution of the study subjects who received ProQuad was as follows: 70.7% White; 10.9% Asian/Pacific; 10.7% African-American; 4.5% Hispanic; 3.0% other; and 0.2% American Indian. The gender distribution of the study subjects who received ProQuad was 53.6% male and 46.4% female.

ProQuad Administered with Pneumococcal 7-valent Conjugate Vaccine and/or Hepatitis A Vaccine, Inactivated

In an open-label clinical trial, 1027 healthy children 12 to 23 months of age were randomized to receive ProQuad administered subcutaneously (dose 1) and pneumococcal 7-valent conjugate vaccine (dose 4) concomitantly (N=510) or non-concomitantly at different clinic visits (N=517). The race distribution of the study subjects was as follows: 65.2% White; 15.1% African-American; 10.0% Hispanic; 6.6% other; and 3.0% Asian/Pacific. The gender distribution of the study subjects was 54.5% male and 45.5% female. Injection-site and systemic adverse reactions observed among recipients of ProQuad administered concomitantly or non-concomitantly with pneumococcal 7-valent conjugate vaccine at a rate of at least 1% are shown in Table 4. No clinically significant differences in adverse reactions were reported between the concomitant and non-concomitant treatment groups [see Clinical Studies (14)].

Table 4: Vaccine-Related Injection-Site and Systemic Adverse Reactions Reported in ≥1% of Children Who Received ProQuad (dose 1) Concomitantly or Non-Concomitantly with PCV7 [PCV7 = Pneumococcal 7-valent conjugate vaccine, dose 4.] (dose 4) at the First Visit (1 to 28 Days Postvaccination)
Adverse Reactions | ProQuad + PCV7 (N=510) (n=498) % | PCV7 (N=258) (n=250) % | ProQuad (N=259) (n=255) %
Injection-Site - ProQuad
Pain [Designates a solicited adverse reaction. Injection-site adverse reactions were solicited only from Days 1 to 5 postvaccination.] | 24.9 | N/A | 24.7
Erythema | 12.4 | N/A | 11.0
Swelling | 10.8 | N/A | 7.5
Bruising | 2.0 | N/A | 1.6
Injection-Site - PCV7
Pain | 30.5 | 29.6 | N/A
Erythema | 21.1 | 24.4 | N/A
Swelling | 17.9 | 20.0 | N/A
Bruising | 1.6 | 1.2 | N/A
Systemic
Fever, [Temperature reported as elevated (≥102°F, oral equivalent) or abnormal.] | 15.5 | 10.0 | 15.3
Measles-like rash | 4.4 | 0.8 | 5.1
Irritability | 3.8 | 3.6 | 3.5
Upper respiratory infection | 1.6 | 0.8 | 1.2
Varicella-like/vesicular rash | 1.6 | 0.0 | 1.2
Diarrhea | 0.8 | 1.2 | 1.2
Vomiting | 0.6 | 0.8 | 1.2
Rash | 0.4 | 0.0 | 1.2
Somnolence | 0.0 | 0.0 | 1.2
N/A = Not applicable.
N = number of subjects vaccinated.
n = number of subjects with safety follow-up.

In an open-label clinical trial, 699 healthy children 12 to 23 months of age were randomized to receive 2 doses of VAQTA (hepatitis A vaccine, inactivated) (N=352) or 2 doses of VAQTA concomitantly with 2 doses of ProQuad administered subcutaneously (N=347) at least 6 months apart. An additional 1101 subjects received 2 doses of VAQTA alone at least 6 months apart (non-randomized), resulting in 1453 subjects receiving 2 doses of VAQTA alone (1101 non-randomized and 352 randomized) and 347 subjects receiving 2 doses of VAQTA concomitantly with ProQuad (all randomized). The race distribution of the study subjects following a dose of ProQuad was as follows: 47.3% White; 42.7% Hispanic; 5.5% other; 2.9% African-American; and 1.7% Asian/Pacific. The gender distribution of the study subjects following a dose of ProQuad was 49.3% male and 50.7% female. Vaccine-related injection-site adverse reactions (days 1 to 5 postvaccination) and systemic adverse events (days 1 to 14 post VAQTA and days 1 to 28 post ProQuad vaccination) observed among recipients of VAQTA and ProQuad administered concomitantly with VAQTA at a rate of at least 1% are shown in Tables 5 and 6, respectively. In addition, among the randomized cohort, in the 14 days after each vaccination, the rates of fever (including all vaccine- and non-vaccine-related reports) were significantly higher in subjects who received ProQuad with VAQTA concomitantly after dose 1 (22.0%) as compared to subjects given dose 1 of VAQTA without ProQuad (10.8%). However, rates of fever were not significantly higher in subjects who received ProQuad with VAQTA concomitantly after dose 2 (12.5%) as compared to subjects given dose 2 of VAQTA without ProQuad (9.4%). In post-hoc analyses, these rates were significantly different for dose 1 (relative risk (RR) 2.03 [95% CI: 1.42, 2.94]), but not dose 2 (RR 1.32 [95% CI: 0.82, 2.13]). Rates of injection-site adverse reactions and other systemic adverse events were lower following a second dose than following the first dose of both vaccines given concomitantly.

Table 5: Vaccine-Related Injection-Site Adverse Reactions Reported in ≥1% of Children Who Received VAQTA or ProQuad Concomitantly with VAQTA 1 to 5 Days After Vaccination with VAQTA or VAQTA and ProQuad
 | Dose 1 |  | Dose 2
Adverse Reactions | VAQTA (N=1453) (n=1412) % | ProQuad + VAQTA (N=347) (n=328) % | VAQTA (N=1301) (n=1254) % | ProQuad + VAQTA (N=292) (n=264) %
Injection-Site - VAQTA
Pain/tenderness [Designates a solicited adverse reaction. Injection-site adverse reactions were solicited only from Days 1 to 5 postvaccination.] | 29.2 | 27.1 | 30.1 | 25.0
Erythema | 13.5 | 12.5 | 14.3 | 11.7
Swelling | 7.1 | 9.1 | 9.0 | 8.0
Injection-site bruising | 1.9 | 2.4 | 1.0 | 0.8
Injection-Site - ProQuad
Pain/tenderness | N/A | 30.5 | N/A | 26.2
Erythema | N/A | 13.4 | N/A | 12.9
Swelling | N/A | 6.7 | N/A | 6.5
Injection-site bruising | N/A | 1.5 | N/A | 0.4
N/A = Not applicable.
N = number of subjects vaccinated.
n = number of subjects with safety follow-up.

Table 6: Vaccine-Related Systemic Adverse Reactions Reported in ≥1% of Children Who Received VAQTA [Systemic adverse events for subjects given VAQTA alone were collected for 14 days postvaccination.] or ProQuad Concomitantly with VAQTA 1 to 14 Days After VAQTA or Vaccination with ProQuad and VAQTA and 1 to 28 Days After Vaccination with ProQuad and VAQTA
Adverse Reactions | Dose 1 |  |  | Dose 2
Adverse Reactions | Days 1 to 14 |  | Days 1 to 28 | Days 1 to 14 |  | Days 1 to 28
Adverse Reactions | VAQTA [Safety follow-up for systemic adverse reactions was 14 days for VAQTA and 28 days for ProQuad + VAQTA.] (N=1453) (n=1412) % | ProQuad + VAQTA (N=347) (n=328) % | ProQuad + VAQTA (N=347) (n=328) % | VAQTA (N=1301) (n=1254) % | ProQuad + VAQTA (N=292) (n=264) % | ProQuad + VAQTA (N=291) (n=263) %
Fever [Designates a solicited adverse reaction.] , [Temperature reported as elevated or abnormal.] | 5.7 | 14.9 | 15.2 | 4.1 | 8.0 | 8.4
Irritability | 5.8 | 7.0 | 7.3 | 3.5 | 5.3 | 5.3
Measles-like rash | 0.0 | 3.4 | 3.4 | 0.0 | 1.1 | 1.1
Rhinorrhea | 0.6 | 2.7 | 3.0 | 0.6 | 1.1 | 2.7
Diarrhea | 1.5 | 1.8 | 2.4 | 1.7 | 0.4 | 0.8
Cough | 0.6 | 2.1 | 2.1 | 0.2 | 0.8 | 1.5
Vomiting | 1.1 | 0.3 | 0.9 | 0.6 | 0.8 | 1.1
N = number of subjects vaccinated.
n = number of subjects with safety follow-up.

In an open-label clinical trial, 653 children 12 to 23 months of age were randomized to receive a first dose of ProQuad administered subcutaneously with VAQTA and pneumococcal 7-valent conjugate vaccine concomitantly (N=330) or a first dose of ProQuad administered subcutaneously and pneumococcal 7-valent conjugate vaccine concomitantly and then vaccinated with VAQTA 6 weeks later (N=323). Approximately 6 months later, subjects received either the second doses of ProQuad and VAQTA concomitantly or the second doses of ProQuad and VAQTA separately. The race distribution of the study subjects was as follows: 60.3% White; 21.6% African-American; 9.5% Hispanic; 7.2% other; 1.1% Asian/Pacific; and 0.3% American Indian. The gender distribution of the study subjects was 50.7% male and 49.3% female. Vaccine-related injection-site and systemic adverse reactions observed among recipients of concomitant ProQuad, VAQTA, and pneumococcal 7-valent conjugate vaccine and ProQuad and pneumococcal 7-valent conjugate vaccine at a rate of at least 1% are shown in Tables 7 and 8. In the 28 days after vaccination with the first dose of ProQuad, the rates of fever (including all vaccine- and non-vaccine-related reports) were comparable in subjects who received the 3 vaccines together (38.6%) as compared with subjects given ProQuad and pneumococcal 7-valent conjugate vaccine (42.7%). The rates of fever in the 28 days following the second dose of ProQuad were also comparable in subjects who received ProQuad and VAQTA together (17.4%) as compared with subjects given ProQuad separately from VAQTA (17.0%). In a post-hoc analysis, these differences were not statistically significant after ProQuad (dose 1) (RR 0.90 [95% CI: 0.75, 1.09]) nor after dose 2 (RR 1.02 [95% CI: 0.70, 1.51]). No clinically significant differences in adverse reactions were reported among treatment groups [see Clinical Studies (14)].

Table 7: Vaccine-Related Injection-Site Adverse Reactions Reported in ≥1% of Children Who Received ProQuad + VAQTA + PCV7 [PCV7 = Pneumococcal 7-valent conjugate vaccine.] Concomitantly or VAQTA Alone Followed by ProQuad + PCV7 Concomitantly (1 to 5 Days After a Dose of ProQuad)
Adverse Reactions | Dose 1 |  | Dose 2
 | VAQTA + ProQuad + PCV7 (N=330) (n=311) % | VAQTA Alone Followed by ProQuad + PCV7 (N=323) (n=302) % | VAQTA + ProQuad (N=273) (n=265) % | VAQTA Alone Followed by ProQuad (N=240) (n=230) %
Injection-Site - ProQuad
Pain/tenderness [Designates a solicited adverse reaction. Injection-site adverse reactions were solicited only from Days 1 to 5 postvaccination at each vaccine injection site.] | 21.2 | 24.2 | 18.1 | 17.0
Erythema | 13.5 | 11.9 | 10.6 | 13.0
Swelling | 7.4 | 10.9 | 8.3 | 11.7
Bruising | 1.9 | 1.3 | 0.8 | 0.4
Injection-Site - VAQTA
Pain/tenderness | 20.6 | 15.3 | 17.5 | 20.3
Erythema | 9.6 | 11.7 | 9.1 | 12.7
Swelling | 6.8 | 9.5 | 6.1 | 7.6
Bruising | 1.3 | 1.1 | 1.1 | 1.6
Rash | 1.0 | 0.0 | 0.4 | 0.4
Injection-Site - PCV7
Pain/tenderness | 25.4 | 27.6 | N/A | N/A
Erythema | 16.4 | 16.6 | N/A | N/A
Swelling | 13.2 | 14.3 | N/A | N/A
Bruising | 0.6 | 1.7 | N/A | N/A
N/A = Not applicable.
N = number of subjects vaccinated.
n = number of subjects with safety follow-up.

Table 8: Vaccine-Related Systemic Adverse Reactions Reported in ≥1% of Children Who Received ProQuad + VAQTA + PCV7 [PCV7 = Pneumococcal 7-valent conjugate vaccine.] Concomitantly, or VAQTA Alone Followed by ProQuad + PCV7 Concomitantly (1 to 28 Days After a Dose of ProQuad)
Adverse Reactions | Dose 1 |  | Dose 2
 | VAQTA + ProQuad + PCV7 (N=330) (n=311) % | VAQTA Alone Followed by ProQuad + PCV7 (N=323) (n=302) % | VAQTA + ProQuad (N=273) (n=265) % | VAQTA Alone Followed by ProQuad (N=240) (n=230) %
Fever [Designates a solicited adverse reaction.] , [Temperature reported as elevated or abnormal.] | 26.4 | 27.2 | 9.1 | 9.6
Irritability | 4.8 | 6.3 | 1.9 | 1.3
Measles-like rash | 2.3 | 4.0 | 0.0 | 0.0
Varicella-like rash | 1.0 | 1.7 | 0.0 | 0.0
Rash (not otherwise specified) | 1.3 | 1.3 | 0.0 | 0.9
Diarrhea | 1.3 | 1.3 | 0.4 | 1.3
Upper respiratory infection | 1.0 | 1.3 | 1.1 | 0.9
Viral infection | 1.0 | 0.7 | 0.0 | 0.0
Rhinorrhea | 0.0 | 0.7 | 1.1 | 0.0
N = number of subjects vaccinated.
n = number of subjects with safety follow-up.

In a randomized open-label clinical trial (NCT00402831), conducted in France, 405 children 12 months through 18 months of age received 2 doses of ProQuad, administered 30 days apart (a non-US licensed interval), by either the intramuscular (n=202) or subcutaneous (n=203) route. In the overall population, 50.9% were male and the median age was 13.3 months. Local and systemic solicited adverse reactions were recorded by parents or guardians using standardized diary cards. Local solicited reactions were recorded for 4 days after vaccination, and systemic solicited adverse reactions were recorded for 28 days after vaccination. In the event that a participant experienced a rash or a mumps-like illness, parents and/or guardians were instructed to contact the investigator for an examination as soon as possible and no later than 72 hours following onset of symptoms. The nature of any rash was characterized by principal investigator either as measles-like, rubella-like, varicella-like or “other”. Study investigators reviewed the diary card with the participant or participant’s legal guardian 30 days and 42 days after dose 1 and dose 2, respectively to ensure consistency with protocol definitions. Tables 9 and 10 below present the frequency of solicited adverse reactions based on the final assessment by the study investigators.

Table 9. Proportion of Participants Reporting Solicited Adverse Reactions Following First Vaccination with ProQuad, by the Intramuscular or Subcutaneous Route
 | INTRAMUSCULAR N=202 % | SUBCUTANEOUS N=203 %
Solicited local injection-site adverse reactions (Days 0 to 4) [Post-dose 1 (0-28 days), there was one episode of an injection-site rubella-like rash and one injection-site varicella-like rash. They were both reported in the subcutaneous group.]
Erythema [Intensity of injection site reaction: mild or ≤2.5 cm; moderate or >2.5 to ≤5.0 cm; severe or >5.0 cm.] | 5.0 | 14.3
Mild | 4.5 | 12.8
Moderate | 0 | 1.5
Severe | 0 | 0
Missing | 0.5 | 0
Pain [Intensity of pain: mild: awareness of symptom but easily tolerated; moderate: definitely acting like something is wrong; severe: extremely distressed or unable to do usual activities.] | 10.9 | 5.9
Mild | 8.9 | 3.9
Moderate | 2.0 | 2.0
Severe | 0 | 0
Swelling | 1.0 | 3.9
Mild | 1.0 | 3.9
Moderate | 0 | 0
Severe | 0 | 0
Solicited systemic adverse reactions (Days 0 to 28)
Measles/Measles-like rash | 0.5 | 2.0
Rubella/Rubella-like rash | 3.0 | 3.0
Varicella/Varicella-like rash | 1.0 | 0.5
Zoster/Zoster-like rash | 0 | 0
Mumps-like illness | 0.5 | 0
Fever (temperature ≥38.0°C) [The percentage of fever is defined within the population who had valid temperature measurements. Three participants in IM group and four participants in SC group do not have temperature measurements and were excluded from the denominator; resulting in N=199 and N=199, respectively.] , [In the IM Group 96.0% of fevers were documented using the rectal route of measurement and 4.0% of fevers were documented only by the axillary route of measurement. In the SC Group 99.3% of fevers were documented using the rectal route of measurement and 0.7% of fevers were documented only by the axillary route of measurement.] | 62.8 | 68.3
38.0-38.5°C | 21.1 | 17.6
>38.5-39.0°C | 18.1 | 21.6
>39.0-39.5°C | 14.1 | 18.1
>39.5-40.0°C | 7.0 | 9.0
>40.0°C | 2.5 | 2.0
N=total number of participants in the group

Table 10. Proportion of Participants Reporting Solicited Adverse Reactions Following Second Vaccination with ProQuad, by the Intramuscular or Subcutaneous Route
 | INTRAMUSCULAR N=201 % | SUBCUTANEOUS N=200 %
Solicited local injection-site adverse reactions (Days 0 to 4) [Post-dose 2 (0-28 days), there was only 1 episode of an injection-site measle-like rash and this was reported in the subcutaneous group.]
Erythema [Intensity of injection site reaction: mild or ≤2.5 cm; moderate or >2.5 to ≤5.0 cm; severe or >5.0 cm.] | 15.4 | 27.0
Mild | 13.9 | 22.5
Moderate | 1.0 | 4.5
Severe | 0 | 0
Missing | 0.5 | 0
Pain [Intensity of pain: mild: awareness of symptom but easily tolerated; moderate: definitely acting like something is wrong; severe: extremely distressed or unable to do usual activities.] | 10.0 | 10.0
Mild | 9.0 | 7.0
Moderate | 0.5 | 3.0
Severe | 0.5 | 0
Swelling | 6.0 | 12.5
Mild | 5.0 | 11.0
Moderate | 1.0 | 1.0
Severe | 0 | 0
Missing | 0 | 0.5% (1/200)
Solicited systemic adverse reactions (Days 0 to 28)
Measles-like rash | 0 | 1.0
Rubella-like rash | 2.0 | 1.0
Varicella-like rash | 0 | 2.0
Zoster-like rash | 0 | 0
Mumps-like illness | 0.5 | 0
Fever (temperature ≥38.0°C) [The percentage of fever is defined within the population who had valid temperature measurements. Five participants in IM group and five participants in SC group did not have temperature measurements and were excluded from the denominator; resulting in N=196 and N=195, respectively.] , [In the IM Group 95.9% of fevers were documented using the rectal route of measurement and 4.1% of fevers were documented only by the axillary route of measurement. In the SC Group 98.9% of fevers were documented using the rectal route of measurement and 1.1% of fevers were documented only by the axillary route of measurement.] | 50.0 | 47.2
38.0-38.5°C | 13.8 | 16.4
>38.5-39.0°C | 18.4 | 10.8
>39.0-39.5°C | 11.2 | 11.3
>39.5-40.0°C | 5.6 | 7.2
>40.0°C | 1.0 | 1.5
N=total number of participants in the group

Unsolicited adverse events (0-28 days post-vaccination 1 and 2) and serious adverse events (day 0 to last visit) were recorded using diary cards supplemented by medical review. Data on unsolicited adverse events were transcribed into the study database during an on-site visit at day 30 and day 42. Serious adverse events occurred at a rate of 1% and 0.5% in each group post-dose 1 and 2, respectively. None of the serious adverse events that occurred were considered related to the study vaccination.

Herpes Zoster

ProQuad and VARIVAX each contain the Oka/Merck varicella virus vaccine strain. Clinical trial data with VARIVAX are therefore, relevant to ProQuad. Overall, 9454 healthy children (12 months to 12 years of age) and 1648 adolescents and adults (13 years of age and older) have been vaccinated with VARIVAX in clinical trials. Eight cases of herpes zoster have been reported in children during 42,556 person-years of follow-up in clinical trials, resulting in a calculated incidence of at least 18.8 cases per 100,000 person-years. The completeness of this reporting has not been determined. One case of herpes zoster has been reported in the adolescent and adult age group during 5410 person-years of follow-up in clinical trials, resulting in a calculated incidence of 18.5 cases per 100,000 person-years. All 9 cases were mild and without sequelae. Two cultures (one child and one adult) obtained from vesicles were positive for wild-type VZV as confirmed by restriction endonuclease analysis {11}. The long-term effect of VARIVAX on the incidence of herpes zoster, particularly in those vaccinees exposed to wild-type varicella, is unknown at present.

In children, the reported rate of herpes zoster in VARIVAX recipients appears not to exceed that previously determined in a population-based study of healthy children who had experienced wild-type varicella {12}. The incidence of herpes zoster in adults who have had wild-type varicella infection is higher than that in children.

6.2 Post-Marketing Experience

The following adverse events have been identified during post-approval use of either the components of ProQuad or ProQuad. Because the events are reported voluntarily from a population of uncertain size, it is not always possible to reliably estimate their frequency or establish a causal relationship to vaccine exposure.

Infections and infestations

Subacute sclerosing panencephalitis, encephalitis, aseptic meningitis, meningitis, measles, atypical measles, pneumonia, respiratory infection, infection, varicella (vaccine strain), influenza, wild-type or vaccine strain herpes zoster, orchitis, epididymitis, cellulitis, skin infection, retinitis, bronchitis, parotitis, sinusitis, impetigo, herpes simplex, candidiasis, rhinitis.

The vaccine virus (Oka/Merck strain) contained in ProQuad may establish latency of varicella zoster virus in immunocompetent individuals, with the potential for later development of herpes zoster.

Cases of encephalitis or meningitis caused by vaccine strain varicella virus have been reported in immunocompromised and immunocompetent individuals previously vaccinated with VARIVAX (same varicella vaccine strain as in ProQuad) months to years after vaccination. Reported cases were commonly associated with preceding or concurrent herpes zoster rash.

Blood and the lymphatic system disorders

Aplastic anemia, thrombocytopenia, regional lymphadenopathy, lymphadenitis.

Immune system disorders

Anaphylaxis and related phenomena such as angioneurotic edema, facial edema, and peripheral edema, anaphylactoid reaction.

Psychiatric disorders

Agitation, apathy, nervousness.

Nervous system disorders

Measles inclusion body encephalitis, acute disseminated encephalomyelitis, transverse myelitis, cerebrovascular accident, encephalopathy, Guillain-Barré syndrome, optic neuritis, Bell’s palsy, polyneuropathy, ataxia, hypersomnia, afebrile convulsions or seizures, febrile seizure, headache, syncope, dizziness, tremor, paresthesia.

Eye disorders

Necrotizing retinitis (in immunocompromised individuals), retrobulbar neuritis, ocular palsies, edema of the eyelid, irritation eye.

Ear and labyrinth disorders

Nerve deafness, ear pain.

Vascular disorders

Extravasation blood.

Respiratory, thoracic and mediastinal disorders

Pneumonitis, pulmonary congestion, wheezing, bronchial spasm, epistaxis, sore throat.

Gastrointestinal disorders

Hematochezia, abdominal pain, mouth ulcer.

Skin and subcutaneous tissue disorders

Stevens-Johnson syndrome, Henoch-Schönlein purpura, erythema multiforme, acute hemorrhagic edema of infancy, purpura, skin induration, panniculitis, pruritus, chronic cutaneous granulomas with rubella vaccine virus detected by biopsy.

Musculoskeletal, connective tissue and bone disorders

Arthritis, arthralgia, pain of the hip, leg, or neck; myalgia; musculoskeletal pain.

General disorders and administration site conditions

Injection-site complaints including wheal and flare, warm to touch, stiffness, warm sensation, inflammation, injection-site hemorrhage, injection-site injury.

Herpes Zoster

The vaccine virus (Oka/Merck strain) contained in ProQuad may establish latency of varicella zoster virus in immunocompetent individuals, with the potential for later development of herpes zoster.

6.3 Post-Marketing Observational Safety Surveillance Study

Safety was evaluated in an observational study that included 69,237 children vaccinated with ProQuad 12 months to 12 years old. A historical comparison group included 69,237 age-, gender-, and date-of-vaccination- (day and month) matched subjects who were given M-M-R II and VARIVAX concomitantly. The primary objective was to assess the incidence of febrile seizures occurring within various time intervals after vaccination in 12- to 60-month-old children who had neither been vaccinated against measles, mumps, rubella, or varicella, nor had a history of the wild-type infections (N=31,298 vaccinated with ProQuad, including 31,043 who were 12 to 23 months old). The incidence of febrile seizures was also assessed in a historical control group of children who had received their first vaccination with M-M-R II and VARIVAX concomitantly (N=31,298, including 31,019 who were 12 to 23 months old). The secondary objective was to assess the general safety of ProQuad in the 30-day period after vaccination in children 12 months to 12 years old.

In pre-licensure clinical studies, an increase in fever was observed 5 to 12 days after vaccination with ProQuad (dose 1) compared to M-M-R II and VARIVAX (dose 1) given concomitantly. In the post-marketing observational surveillance study, results from the primary safety analysis revealed an approximate two-fold increase in the risk of febrile seizures in the same 5 to 12 day timeframe after vaccination with ProQuad (dose 1). The incidence of febrile seizures 5 to 12 days after ProQuad (dose 1) (0.70 per 1000 children) was higher than that in children receiving M-M-R II and VARIVAX concomitantly (0.32 per 1000 children) [RR 2.20, 95% confidence interval (CI): 1.04, 4.65]. The incidence of febrile seizures 0 to 30 days after ProQuad (dose 1) (1.41 per 1000 children) was similar to that observed in children receiving M-M-R II and VARIVAX concomitantly [RR 1.10 (95% CI: 0.72, 1.69)]. See Table 11. General safety analyses revealed that the risks of fever (RR=1.89; 95% CI: 1.67, 2.15) and skin eruption (RR=1.68; 95% CI: 1.07, 2.64) were significantly higher after ProQuad (dose 1) compared with those who received concomitant first doses of M-M-R II and VARIVAX, respectively. All medical events that resulted in hospitalization or emergency room visits were compared between the group given ProQuad and the historical comparison group, and no other safety concerns were identified in this study.

Table 11: Confirmed Febrile Seizures Days 5 to 12 and 0 to 30 After Vaccination with ProQuad (dose 1) Compared to Concomitant Vaccination with M-M-R II and VARIVAX (dose 1) in Children 12 to 60 Months of Age
Time Period | ProQuad cohort (N=31,298) |  | MMR+V cohort (N=31,298) |  | Relative risk (95% CI)
Time Period | n | Incidence per 1000 | n | Incidence per 1000 | Relative risk (95% CI)
5 to 12 Days | 22 | 0.70 | 10 | 0.32 | 2.20 (1.04, 4.65)
0 to 30 Days | 44 | 1.41 | 40 | 1.28 | 1.10 (0.72, 1.69)

In this observational post-marketing study, no case of febrile seizure was observed during the 5 to 12 day postvaccination time period among 26,455 children who received ProQuad as a second dose of M-M-R II and VARIVAX. In addition, detailed general safety data were available from more than 25,000 children who received ProQuad as a second dose of M-M-R II and VARIVAX, most of them (95%) between 4 and 6 years of age, and an analysis of these data by an independent, external safety monitoring committee did not identify any specific safety concern.

7 DRUG INTERACTIONS

7.1 Immunosuppressive Drugs

Do not administer ProQuad vaccine to individuals who are immunosuppressed due to medical therapy. Vaccination with ProQuad vaccine can result in disseminated disease due to vaccine viruses in individuals on immunosuppressive drugs [see Contraindications (4.2)].

7.2 Immune Globulins and Other Blood Products

Administration of immune globulins and other blood products concurrently with ProQuad vaccine may interfere with the expected immune response [see Warnings and Precautions (5.7)] {9-11}. The U.S. Centers for Disease Control and Prevention (CDC) has specific recommendations for intervals between administration of antibody containing products and live virus vaccines.

7.3 Salicylates

Reye syndrome has been reported following the use of salicylates during wild-type varicella infection. Vaccine recipients should avoid use of salicylates for 6 weeks after vaccination with ProQuad [see Warnings and Precautions (5.8) and Patient Counseling Information (17)].

7.4 Drug/Laboratory Test Interactions

Live, attenuated measles, mumps, and rubella virus vaccines given individually may result in a temporary depression of tuberculin skin sensitivity. Therefore, if a tuberculin test is to be done, it should be administered either any time before, simultaneously with, or at least 4 to 6 weeks after ProQuad.

7.5 Use with Other Vaccines

At least 1 month should elapse between a dose of a measles-containing vaccine and a dose of ProQuad, and at least 3 months should elapse between administration of 2 doses of ProQuad or varicella-containing vaccines.

ProQuad may be administered concomitantly with Haemophilus influenzae type b conjugate (meningococcal protein conjugate) and hepatitis B (recombinant). Additionally, ProQuad may be administered concomitantly with pneumococcal 7-valent conjugate vaccine, and/or hepatitis A (inactivated) vaccines [see Clinical Studies (14)].

8 USE IN SPECIFIC POPULATIONS

8.1 Pregnancy

Risk Summary

ProQuad vaccine contains live attenuated measles, mumps, rubella and varicella viruses. The vaccine is contraindicated for use in pregnant women because infection during pregnancy with the wild-type viruses is associated with maternal and fetal adverse outcomes.

Increased rates of spontaneous abortion, stillbirth, premature delivery and congenital defects have been observed following infection with wild-type measles during pregnancy {13,14}. Wild-type mumps infection during the first trimester of pregnancy may increase the rate of spontaneous abortion.

Infection with wild-type rubella during pregnancy can lead to miscarriage or stillbirth. If rubella infection occurs during the first trimester of pregnancy, it can result in severe congenital defects, Congenital Rubella Syndrome (CRS). Post-marketing surveillance has identified one case of CRS following inadvertent vaccination of a pregnant woman with a measles, mumps, and rubella virus containing vaccine from an unknown manufacturer (see Data) {18}.

Wild-type varicella, if acquired during pregnancy, can sometimes cause congenital varicella syndrome.

All pregnancies have a risk of birth defect, loss, or other adverse outcomes. In the US general population, the estimated background risk of major birth defects and miscarriage in clinically recognized pregnancies is 2% to 4%, and 15% to 20%, respectively {15,16}.

Data

Human Data

A cumulative assessment of post-marketing reports from 01 April 1978 through 31 December 2018 for a vaccine containing the measles, mumps, and rubella components of ProQuad, identified 796 reports of inadvertent administration occurring 30 days before or at any time during pregnancy with known pregnancy outcomes. Of the prospectively followed pregnancies for whom the timing of vaccination was known, 425 women were vaccinated during the 30 days prior to conception through the second trimester. The outcomes for these 425 prospectively followed pregnancies included 16 infants with major birth defects, 4 cases of fetal death and 50 cases of miscarriage; no abnormalities compatible with CRS were identified.

The CDC established the Vaccine in Pregnancy registry (1971-1989) of women who had received rubella virus vaccines within 3 months before or after conception. Data on 1221 inadvertently vaccinated pregnant women demonstrated no evidence of an increase in fetal abnormalities or cases of CRS in the enrolled women {17}.

Post-marketing surveillance has identified a case of CRS associated with a rubella virus strain belonging to the genotype that includes the rubella virus strain Wistar RA 27/3 contained in ProQuad. The infant with CRS was born to a pregnant woman who was inadvertently vaccinated at 5 weeks gestation with a measles, mumps, and rubella virus containing vaccine from an unknown manufacturer {18}.

Mumps vaccine virus has been shown to infect the placenta {19}, but there is no evidence that it causes congenital malformations or disease in the fetus or infant.

8.2 Lactation

Risk Summary

It is not known whether varicella, measles, or mumps vaccine virus is excreted in human milk. Studies have shown that lactating postpartum women vaccinated with live rubella vaccine may secrete the virus in breast milk and transmit it to breastfed infants [see Warnings and Precautions (5.6)] {20,21}.

The developmental and health benefits of breastfeeding should be considered along with the mother's clinical need for ProQuad, and any potential adverse effects on the breastfed child from ProQuad or from the underlying maternal condition. For preventive vaccines, the underlying maternal condition is susceptibility to disease prevented by the vaccine.

8.4 Pediatric Use

Do not administer ProQuad to infants younger than 12 months of age or to children 13 years and older. Safety and effectiveness of ProQuad in infants younger than 12 months of age and in children 13 years and older have not been established [see Clinical Studies (14)].

8.5 Geriatric Use

ProQuad is not indicated for use in the geriatric population (≥age 65).

11 DESCRIPTION

ProQuad (Measles, Mumps, Rubella and Varicella Virus Vaccine Live) is a combined, attenuated, live virus vaccine containing measles, mumps, rubella, and varicella viruses. ProQuad is a sterile lyophilized preparation of (1) the components of M-M-R II (Measles, Mumps, and Rubella Virus Vaccine Live): Measles Virus Vaccine Live, a more attenuated line of measles virus, derived from Enders' attenuated Edmonston strain and propagated in chick embryo cell culture; Mumps Virus Vaccine Live, the Jeryl Lynn™ (B level) strain of mumps virus propagated in chick embryo cell culture; Rubella Virus Vaccine Live, the Wistar RA 27/3 strain of live attenuated rubella virus propagated in WI-38 human diploid lung fibroblasts; and (2) Varicella Virus Vaccine Live (Oka/Merck), the Oka/Merck strain of varicella-zoster virus propagated in MRC-5 cells. The cells, virus pools, bovine serum, and recombinant human albumin used in manufacturing are all tested to provide assurance that the final product is free of potential adventitious agents.

ProQuad, when reconstituted as directed, is a sterile injectable suspension for intramuscular or subcutaneous use. Each approximately 0.5 mL dose contains not less than 3.00 log10 TCID50 of measles virus; 4.30 log10 TCID50 of mumps virus; 3.00 log10 TCID50 of rubella virus; and not less than 3.99 log10 PFU of Oka/Merck varicella virus.

After reconstitution, each 0.5 mL dose of the vaccine also contains 21 mg of sucrose, 11 mg of hydrolyzed gelatin, 2.4 mg of sodium chloride, 1.8 mg of sorbitol, 0.40 mg of monosodium L-glutamate, 0.34 mg of sodium phosphate dibasic, 0.31 mg of recombinant human albumin, 0.17 mg of sodium bicarbonate, 72 mcg of potassium phosphate monobasic, 60 mcg of potassium chloride; 36 mcg of potassium phosphate dibasic; and residual components from the manufacturing process: MRC-5 cells including DNA and protein; <16 mcg of neomycin, ≤0.5 mcg of bovine calf serum, and other buffer and media ingredients. The product contains no preservative.

12 CLINICAL PHARMACOLOGY

12.1 Mechanism of Action

ProQuad has been shown to induce measles-, mumps-, rubella-, and varicella-specific immunity, which is thought to be the mechanism by which it protects against these four childhood diseases.

The efficacy of ProQuad was established through the use of immunological correlates for protection against measles, mumps, rubella, and varicella. Results from efficacy studies or field effectiveness studies that were previously conducted for the component vaccines were used to define levels of serum antibodies that correlated with protection against measles, mumps, and rubella. Also, in previous studies with varicella vaccine, antibody responses against varicella virus ≥5 gpELISA units/mL in a glycoprotein enzyme-linked immunosorbent assay (gpELISA) (not commercially available) similarly correlated with long-term protection. In these efficacy studies, the clinical endpoint for measles and mumps was a clinical diagnosis of either disease confirmed by a 4-fold or greater rise in serum antibody titers between either postvaccination or acute and convalescent titers; for rubella, a 4-fold or greater rise in antibody titers with or without clinical symptoms of rubella; and for varicella, varicella-like rash that occurred >42 days postvaccination and for which varicella was not excluded by either viral cultures of the lesion or serological tests. Specific laboratory evidence of varicella either by serology or culture was not required to confirm the diagnosis of varicella. Clinical studies with a single dose of ProQuad have shown that vaccination elicited rates of antibody responses against measles, mumps, and rubella that were similar to those observed after vaccination with a single dose of M-M-R II [see Clinical Studies (14)] and seroresponse rates for varicella virus were similar to those observed after vaccination with a single dose of VARIVAX [see Clinical Studies (14)]. The duration of protection from measles, mumps, rubella, and varicella infections after vaccination with ProQuad is unknown.

12.6 Persistence of Antibody Responses after Vaccination

The persistence of antibody at 1 year after vaccination was evaluated in a subset of 2107 children enrolled in the clinical trials. Antibody was detected in 98.9% (1722/1741) for measles, 96.7% (1676/1733) for mumps, 99.6% (1796/1804) for rubella, and 97.5% (1512/1550) for varicella (≥5 gpELISA units/mL) of vaccinees following a single dose of ProQuad.

Experience with M-M-R II demonstrates that neutralizing and ELISA antibodies to measles, mumps, and rubella viruses are still detectable in 95-100%, 74-91%, and 90-100% of individuals respectively, 11 to 13 years after primary vaccination series {22-26}. Varicella antibodies were present for up to ten years postvaccination in most of the individuals tested who received 1 dose of VARIVAX.

13 NONCLINICAL TOXICOLOGY

13.1 Carcinogenesis, Mutagenesis, Impairment of Fertility

ProQuad has not been evaluated for its carcinogenic, mutagenic, or teratogenic potential, or its potential to impair fertility.

14 CLINICAL STUDIES

Formal studies to evaluate the clinical efficacy of ProQuad have not been performed.

Efficacy of the measles, mumps, rubella, and varicella components of ProQuad was previously established in a series of clinical studies with the monovalent vaccines. A high degree of protection from infection was demonstrated in these studies {29-36}.

Immunogenicity in Children 12 Months to 6 Years of Age

Prior to licensure, immunogenicity was studied in 5845 healthy children 12 months to 6 years of age with a negative clinical history of measles, mumps, rubella, and varicella who participated in 5 randomized clinical trials. The immunogenicity of ProQuad administered subcutaneously was similar to that of its individual component vaccines (M-M-R II and VARIVAX), which are currently used in routine vaccination.

The presence of detectable antibody was assessed by an appropriately sensitive enzyme-linked immunosorbent assay (ELISA) for measles, mumps (wild-type and vaccine-type strains), and rubella, and by gpELISA for varicella. For evaluation of vaccine response rates, a positive result in the measles ELISA corresponded to measles antibody concentrations of ≥255 mIU/mL when compared to the WHO II (66/202) Reference Immunoglobulin for Measles.

Children were positive for mumps antibody if the antibody level was ≥10 ELISA units/mL. A positive result in the rubella ELISA corresponded to concentrations of ≥10 IU rubella antibody/mL when compared to the WHO International Reference Serum for Rubella; children with varicella antibody levels ≥5 gpELISA units/mL were considered to be seropositive since a response rate based on ≥5 gpELISA units/mL has been shown to be highly correlated with long-term protection.

Immunogenicity in Children 12 to 23 Months of Age After a Single Dose

In 4 randomized clinical trials, 5446 healthy children 12 to 23 months of age were administered ProQuad subcutaneously, and 2038 children were vaccinated with M-M-R II and VARIVAX given concomitantly at separate injection sites. Subjects enrolled in each of these trials had a negative clinical history, no known recent exposure, and no vaccination history for varicella, measles, mumps, and rubella. Children were excluded from study participation if they had an immune impairment or had a history of allergy to components of the vaccine(s). Except for in 1 trial [see ProQuad Administered with Diphtheria and Tetanus Toxoids and Acellular Pertussis Vaccine Adsorbed (DTaP) and Haemophilus influenzae type b Conjugate (Meningococcal Protein Conjugate) and Hepatitis B (Recombinant) Vaccine below], no concomitant vaccines were permitted during study participation. The race distribution of the study subjects across these studies following a first dose of ProQuad was as follows: 66.3% White; 12.7% African-American; 9.9% Hispanic; 6.7% Asian/Pacific; 4.2% other; and 0.2% American Indian. The gender distribution of the study subjects across these studies following a first dose of ProQuad was 52.6% male and 47.4% female. A summary of combined immunogenicity results 6 weeks following administration of a single dose of ProQuad or M-M-R II and VARIVAX is shown in Table 12. These results were similar to the immune response rates induced by concomitant administration of single doses of M-M-R II and VARIVAX at separate injection sites (lower bound of the 95% CI for the risk difference in measles, mumps, and rubella seroconversion rates were >-5.0 percentage points and the lower bound of the 95% CI for the risk difference in varicella seroprotection rates was either >-15 percentage points [one study] or >-10.0 percentage points [three studies]).

Table 12: Summary of Combined Immunogenicity Results 6 Weeks Following the Administration of a Single Dose of ProQuad (Varicella Virus Potency ≥3.97 log10 PFU) or M-M-R II and VARIVAX (Per-Protocol Population)
Group | Antigen | n | Observed Response Rate (95% CI) | Observed GMT (95% CI)
ProQuad (N=5446 [Includes ProQuad + Placebo followed by ProQuad (Visit 1) (Protocol 009), ProQuad Middle and High Doses (Visit 1) (Protocol 011), ProQuad (Lot 1, Lot 2, Lot 3) (Protocol 012), both the Concomitant and Non-concomitant groups (Protocol 013).]) | Varicella | 4381 | 91.2% (90.3%, 92.0%) | 15.5 (15.0, 15.9)
ProQuad (N=5446 [Includes ProQuad + Placebo followed by ProQuad (Visit 1) (Protocol 009), ProQuad Middle and High Doses (Visit 1) (Protocol 011), ProQuad (Lot 1, Lot 2, Lot 3) (Protocol 012), both the Concomitant and Non-concomitant groups (Protocol 013).]) | Measles | 4733 | 97.4% (96.9%, 97.9%) | 3124.9 (3038.9, 3213.3)
ProQuad (N=5446 [Includes ProQuad + Placebo followed by ProQuad (Visit 1) (Protocol 009), ProQuad Middle and High Doses (Visit 1) (Protocol 011), ProQuad (Lot 1, Lot 2, Lot 3) (Protocol 012), both the Concomitant and Non-concomitant groups (Protocol 013).]) | Mumps (OD cutoff) [The mumps antibody response was assessed by a vaccine-strain ELISA in Protocols 009 and 011 and by a wild-type ELISA in Protocols 012 and 013. In the former assay, the serostatus was based on the OD cutoff of the assay. In the latter assay, 10 mumps ELISA units was used as the serostatus cutoff.] | 973 | 98.8% (97.9%, 99.4%) | 105.3 (98.0, 113.1)
ProQuad (N=5446 [Includes ProQuad + Placebo followed by ProQuad (Visit 1) (Protocol 009), ProQuad Middle and High Doses (Visit 1) (Protocol 011), ProQuad (Lot 1, Lot 2, Lot 3) (Protocol 012), both the Concomitant and Non-concomitant groups (Protocol 013).]) | Mumps (wild-type ELISA) | 3735 | 95.8% (95.1%, 96.4%) | 93.1 (90.2, 96.0)
ProQuad (N=5446 [Includes ProQuad + Placebo followed by ProQuad (Visit 1) (Protocol 009), ProQuad Middle and High Doses (Visit 1) (Protocol 011), ProQuad (Lot 1, Lot 2, Lot 3) (Protocol 012), both the Concomitant and Non-concomitant groups (Protocol 013).]) | Rubella | 4773 | 98.5% (98.1%, 98.8%) | 91.8 (89.6, 94.1)
M-M-R II + VARIVAX (N=2038) | Varicella | 1417 | 94.1% (92.8%, 95.3%) | 16.6 (15.9, 17.4)
M-M-R II + VARIVAX (N=2038) | Measles | 1516 | 98.2% (97.4%, 98.8%) | 2239.6 (2138.3, 2345.6)
M-M-R II + VARIVAX (N=2038) | Mumps (OD cutoff) | 501 | 99.4% (98.3%, 99.9%) | 87.5 (79.7, 96.0)
M-M-R II + VARIVAX (N=2038) | Mumps (wild-type ELISA) | 1017 | 98.0% (97.0%, 98.8%) | 90.8 (86.2, 95.7)
M-M-R II + VARIVAX (N=2038) | Rubella | 1528 | 98.5% (97.7%, 99.0%) | 102.2 (97.8, 106.7)
n = Number of per-protocol subjects with evaluable serology.
CI = Confidence interval.
GMT = Geometric mean titer.
ELISA = Enzyme-linked immunosorbent assay.
PFU = Plaque-forming units.
OD = Optical density.

Immunogenicity in Children 15 to 31 Months of Age After a Second Dose of ProQuad

In 2 of the 4 randomized clinical trials described above, a subgroup (N=1035) of the 5446 children administered a single dose of ProQuad subcutaneously were administered a second dose of ProQuad subcutaneously, approximately 3 to 9 months after the first dose. Children were excluded from receiving a second dose of ProQuad if they were recently exposed to or developed varicella, measles, mumps, and/or rubella prior to receipt of the second dose. No concomitant vaccines were administered to these children. The race distribution across these studies following a second dose of ProQuad was as follows: 67.3% White; 14.3% African-American; 8.3% Hispanic; 5.4% Asian/Pacific; 4.4% other; 0.2% American Indian; and 0.10% mixed. The gender distribution of the study subjects across these studies following a second dose of ProQuad was 50.4% male and 49.6% female. A summary of immune responses following a second dose of ProQuad is presented in Table 13. Results from this study showed that 2 doses of ProQuad administered at least 3 months apart elicited a positive antibody response to all four antigens in greater than 98% of subjects. The geometric mean titers (GMTs) following the second dose of ProQuad increased approximately 2-fold each for measles, mumps, and rubella, and approximately 41-fold for varicella.

Table 13: Summary of Immune Response to a First and Second Dose of ProQuad in Subjects <3 Years of Age Who Received ProQuad with a Varicella Virus Dose ≥3.97 Log10 PFU [Includes the following treatment groups: ProQuad + Placebo followed by ProQuad (Visit 1) (Protocol 009) and ProQuad (Middle and High Dose) (Protocol 011).]
 |  | Dose 1 N=1097 |  |  | Dose 2 N=1097
 | Serostatus Cutoff/ |  | Observed Response Rate | Observed GMT |  | Observed Response Rate | Observed GMT
Antigen | Response Criteria | n | (95% CI) | (95% CI) | n | (95% CI) | (95% CI)
Measles | ≥120 mIU/mL [Samples from Protocols 009 and 011 were assayed in the legacy format Measles ELISA, which reported antibody titers in Measles ELISA units. To convert titers from ELISA units to mIU/mL, titers for these 2 protocols were divided by 0.1025. The lowest measurable titer postvaccination is 207.5 mIU/mL. The response rate for measles in the legacy format is the percent of subjects with a negative baseline measles antibody titer, as defined by the optical density (OD) cutoff, with a postvaccination measles antibody titer ≥207.5 mIU/mL. Samples from Protocols 009 and 011 were assayed in the legacy format Rubella ELISA, which reported antibody titers in Rubella ELISA units. To convert titers from ELISA units to IU/mL, titers for these 2 protocols were divided by 1.28.] | 915 | 98.1% (97.0%, 98.9%) | 2956.8 (2786.3, 3137.7) | 915 | 99.5% (98.7%, 99.8%) | 5958.0 (5518.9, 6432.1)
 | ≥255 mIU/mL | 943 | 97.8% (96.6%, 98.6%) | 2966.0 (2793.4, 3149.2) | 943 | 99.4% (98.6%, 99.8%) | 5919.3 (5486.2, 6386.6)
Mumps | ≥OD Cutoff (ELISA antibody units) | 920 | 98.7% (97.7%, 99.3%) | 106.7 (99.1, 114.8) | 920 | 99.9% (99.4%, 100%) | 253.1 (237.9, 269.2)
Rubella | ≥10 IU/mL | 937 | 97.7% (96.5%, 98.5%) | 91.1 (85.9, 96.6) | 937 | 98.3% (97.2%, 99.0%) | 158.8 (149.1, 169.2)
Varicella | <1.25 to ≥5 gpELISA units | 864 | 86.6% (84.1%, 88.8%) | 11.6 (10.9, 12.3) | 864 | 99.4% (98.7%, 99.8%) | 477.5 (437.8, 520.7)
 | ≥OD Cutoff (gpELISA units) | 695 | 87.2% (84.5%, 89.6%) | 11.6 (10.9, 12.4) | 695 | 99.4% (98.5%, 99.8%) | 478.7 (434.8, 527.1)
ProQuad (Middle Dose) = ProQuad containing a varicella virus dose of 3.97 log10 PFU.
ProQuad (High Dose) = ProQuad containing a varicella virus dose of 4.25 log10 PFU.
ELISA = Enzyme-linked immunosorbent assay.
gpELISA = Glycoprotein enzyme-linked immunosorbent assay.
N = Number vaccinated at baseline.
n = Number of subjects who were per-protocol Postdose 1 and Postdose 2 and satisfied the given prevaccination serostatus cutoff.
CI = Confidence interval.
GMT = Geometric mean titer.
PFU = Plaque-forming units.

Immunogenicity in Children 4 to 6 Years of Age Who Received a First Dose of ProQuad After Primary Vaccination With M-M-R II and VARIVAX

In a clinical trial, 799 healthy 4- to 6-year-old children who had received M-M-R II and VARIVAX at least 1 month prior to study entry were randomized to receive ProQuad subcutaneously and placebo (N=399), M-M-R II and placebo concomitantly at separate injection sites (N=205), or M-M-R II and VARIVAX concomitantly at separate injection sites (N=195). Children were eligible if they were previously administered primary doses of M-M-R II and VARIVAX, either concomitantly or non-concomitantly, at 12 months of age or older. Children were excluded if they were recently exposed to measles, mumps, rubella, and/or varicella, had an immune impairment, or had a history of allergy to components of the vaccine(s). No concomitant vaccines were permitted during study participation [see Adverse Reactions (6.1) for ethnicity and gender information].

A summary of antibody responses to measles, mumps, rubella, and varicella at 6 weeks postvaccination in subjects who had previously received M-M-R II and VARIVAX is shown in Table 14. Results from this study showed that a first dose of ProQuad after primary vaccination with M-M-R II and VARIVAX elicited a positive antibody response to all four antigens in greater than 98% of subjects. Postvaccination GMTs for recipients of ProQuad were similar to those following a second dose of M-M-R II and VARIVAX administered concomitantly at separate injection sites (the lower bound of the 95% CI around the fold difference in measles, mumps, rubella, and varicella GMTs excluded 0.5). Additionally, GMTs for measles, mumps, and rubella were similar to those following a second dose of M-M-R II given concomitantly with placebo (the lower bound of the 95% CI around the fold difference for the comparison of measles, mumps, and rubella GMTs excluded 0.5).

Table 14: Summary of Antibody Responses to Measles, Mumps, Rubella, and Varicella at 6 Weeks Postvaccination in Subjects 4 to 6 Years of Age Who Had Previously Received M-M-R II and VARIVAX (Per-Protocol Population)
Group Number |  | GMT (95% CI) | Seropositivity Rate (95% CI) | % ≥4-Fold Rise in Titer (95% CI) | Geometric Mean Fold Rise (95% CI)
(Description) | n | Measles [Measles GMTs are reported in mIU/mL; seropositivity corresponds to ≥120 mIU/mL.]
Group 1 (N=399) | 367 | 1985.9 | 100% | 4.9% | 1.21
(ProQuad + placebo) |  | (1817.6, 2169.9) | (99.0%, 100%) | (2.9%, 7.6%) | (1.13, 1.30)
Group 2 (N=205) | 185 | 2046.9 | 100% | 4.3% | 1.28
(M-M-R II + placebo) |  | (1815.2, 2308.2) | (98.0%, 100%) | (1.9%, 8.3%) | (1.17, 1.40)
Group 3 (N=195) | 171 | 2084.3 | 99.4% | 4.7% | 1.31
(M-M-R II + VARIVAX) |  | (1852.3, 2345.5) | (96.8%, 100%) | (2.0%, 9.0%) | (1.17, 1.46)
 |  | Mumps [Mumps GMTs are reported in mumps Ab units/mL; seropositivity corresponds to ≥10 Ab units/mL.]
Group 1 (N=399) | 367 | 206.0 | 99.5% | 27.2% | 2.43
(ProQuad + placebo) |  | (188.2, 225.4) | (98.0%, 99.9%) | (22.8%, 32.1%) | (2.19, 2.69)
Group 2 (N=205) | 185 | 308.5 | 100% | 41.1% | 3.69
(M-M-R II + placebo) |  | (269.6, 352.9) | (98.0%, 100%) | (33.9%, 48.5%) | (3.14, 4.32)
Group 3 (N=195) | 171 | 295.9 | 100% | 41.5% | 3.36
(M-M-R II + VARIVAX) |  | (262.5, 333.5) | (97.9%, 100%) | (34.0%, 49.3%) | (2.84, 3.97)
 |  | Rubella [Rubella titers obtained by the legacy format were converted to their corresponding titers in the modified format. Rubella serostatus was determined after the conversion to IU/mL: seropositivity corresponds to ≥10 IU/mL.]
Group 1 (N=399) | 367 | 217.3 | 100% | 32.7% | 3.00
(ProQuad + placebo) |  | (200.1, 236.0) | (99.0%, 100%) | (27.9%, 37.8%) | (2.72, 3.31)
Group 2 (N=205) | 185 | 174.0 | 100% | 31.9% | 2.81
(M-M-R II + placebo) |  | (157.3, 192.6) | (98.0%, 100%) | (25.2%, 39.1%) | (2.41, 3.27)
Group 3 (N=195) | 171 | 154.1 | 99.4% | 26.9% | 2.47
(M-M-R II + VARIVAX) |  | (138.9, 170.9) | (96.8%, 100%) | (20.4%, 34.2%) | (2.17, 2.81)
 |  | Varicella [Varicella GMTs are reported in gpELISA units/mL; seropositivity rate is reported by % of subjects with postvaccination antibody titers ≥5 gpELISA units/mL. Percentages are calculated as the number of subjects who met the criterion divided by the number of subjects contributing to the per-protocol analysis.]
Group 1 (N=399) | 367 | 322.2 | 98.9% | 80.7% | 12.43
(ProQuad + placebo) |  | (278.9, 372.2) | (97.2%, 99.7%) | (76.2%, 84.6%) | (10.63, 14.53)
Group 2 (N=205) (M-M-R II + placebo) | 185 | N/A | N/A | N/A | N/A
Group 3 (N=195) | 171 | 209.3 | 99.4% | 71.9% | 8.50
(M-M-R II + VARIVAX) |  | (171.2, 255.9) | (96.8%, 100%) | (64.6%, 78.5%) | (6.69, 10.81)
gpELISA = Glycoprotein enzyme-linked immunosorbent assay; ELISA = Enzyme-linked immunosorbent assay; CI = Confidence interval; GMT = Geometric mean titer; N/A = Not applicable; N = Number of subjects vaccinated; n = number of subjects in the per-protocol analysis.

Immunogenicity Following 2 Doses of ProQuad Administered Intramuscularly or Subcutaneously

In an open label clinical trial (NCT00402831) 405 children 12 through 18 months of age received two doses of ProQuad, administered 30 days apart (a non-US licensed interval), either intramuscularly (n=202) or subcutaneously (n=203). Antibody responses to measles, mumps, rubella and varicella viruses were measured by ELISAs using sera obtained 30 days post-dose 1, and 6-weeks post-dose 2. For anti-measles virus, anti-mumps virus, anti-rubella virus and anti-varicella virus, seroresponse rates were defined as the percentage of children seronegative at baseline who achieved antibody titers above the respective seroresponse threshold for each assay 30 days post-dose 1 and 6 weeks post-dose 2. Seroresponse thresholds were defined as 255 mIU/mL, 10 EU/mL, 10 IU/mL and 5 gpELISA units for anti-measles virus, anti-mumps virus, anti-rubella virus and anti-varicella virus antibodies, respectively after each dose. For each vaccine antigen at least 87% of enrolled children were seronegative at baseline.

The seroresponse rates to measles, mumps, and varicella viruses after dose 1 were noninferior in the intramuscular group compared to the subcutaneous group in a post hoc analysis (lower bound of the 95% confidence interval for the difference in seroresponse rates [intramuscular group minus subcutaneous group] ≥-5%). The seroresponse rate to rubella virus narrowly missed meeting the criterion for noninferiority (lower bounds of the 95% CI for the difference in seroresponse rate -5.5%). For measles, mumps, rubella, and varicella antigens, the lower bound of the 95% CI of the seroresponse rate was ˃90% after intramuscular administration. The proportions of children achieving antibody titers above the seroresponse thresholds for measles, mumps, rubella and varicella viruses after dose 1 were as follows: 100%, 97.4%, 98.4%, and 98.6%, respectively, in the intramuscular group and 97.3%, 91.3%, 100%, and 98.5%, respectively, in the subcutaneous group.

Immunogenicity Following Concomitant Use with Other Vaccines

ProQuad with Pneumococcal 7-valent Conjugate Vaccine and/or VAQTA

In a clinical trial, 1027 healthy children 12 to 15 months of age were randomized to receive ProQuad subcutaneously and pneumococcal 7-valent conjugate vaccine concomitantly (N=510) at separate injection sites or ProQuad administered subcutaneously and pneumococcal 7-valent conjugate vaccine non-concomitantly (N=517) at separate clinic visits [see Adverse Reactions (6.1) for ethnicity and gender information]. The statistical analysis of non-inferiority in antibody response rates to measles, mumps, rubella, and varicella at 6 weeks postvaccination for subjects are shown in Table 15. In the per-protocol population, seroconversion rates were not inferior in children given ProQuad and pneumococcal 7-valent conjugate vaccine concomitantly when compared to seroconversion rates seen in children given these vaccines non-concomitantly for measles, mumps, and rubella. In children with baseline varicella antibody titers <1.25 gpELISA units/mL, the varicella seroprotection rates were not inferior when rates after concomitant and non-concomitant vaccination were compared 6 weeks postvaccination. Statistical analysis of non-inferiority in GMTs to S. pneumoniae serotypes at 6 weeks postvaccination are shown in Table 16. Geometric mean antibody titers (GMTs) for S. pneumoniae types 4, 6B, 9V, 14, 18C, 19F, and 23F were not inferior when antibody titers in the concomitant and non-concomitant groups were compared 6 weeks postvaccination.

Table 15: Statistical Analysis of Non-Inferiority in Antibody Response Rates to Measles, Mumps, Rubella, and Varicella at 6 Weeks Postvaccination for Subjects Initially Seronegative to Measles, Mumps, or Rubella, or With Varicella Antibody Titer <1.25 gpELISA units at Baseline in the ProQuad + PCV7 [PCV7 = Pneumococcal 7-valent conjugate vaccine. Seronegative defined as baseline measles antibody titer <255 mIU/mL for measles, baseline mumps antibody titer <10 ELISA Ab units/mL for mumps, and baseline rubella antibody titer <10 IU/mL for rubella.] Treatment Group and the ProQuad Followed by PCV7 Control Group (Per-Protocol Analysis)
 | ProQuad + PCV7 (N=510) |  | ProQuad followed by PCV7 (N=259) |  | Difference
Assay Parameter | n | Estimated Response [Estimated responses and their differences were based on statistical analysis models adjusting for study center.] | n | Estimated Response | (percentage points), [ProQuad + PCV7 - ProQuad followed by PCV7. The conclusion of non-inferiority is based on the lower bound of the 2-sided 95% CI on the risk difference being greater than -10 percentage points (i.e., excluding a decrease equal to or more than the prespecified criterion of 10.0 percentage points). This indicates that the difference is statistically significantly less than the prespecified clinically relevant decrease of 10.0 percentage points at the 1-sided alpha = 0.025 level.] (95% CI)
Measles % ≥255 mIU/mL | 406 | 97.3% | 204 | 99.5% | -2.2 (-4.6, 0.2)
Mumps % ≥10 Ab units/mL | 403 | 96.6% | 208 | 98.6% | -1.9 (-4.5, 1.0)
Rubella % ≥10 IU/mL | 377 | 98.7% | 195 | 97.9% | 0.9 (-1.3, 4.1)
Varicella % ≥5 gpELISA units/mL | 379 | 92.5% | 192 | 87.9% | 4.5 (-0.4, 10.4)
N = Number of subjects vaccinated in each treatment group.
n = Number of subjects with measles antibody titer <255 mIU/mL, mumps antibody titer <10 ELISA Ab units/mL, rubella antibody titer <10 IU/mL, or varicella antibody titer <1.25 gpELISA units/mL at baseline and with postvaccination serology contributing to the per-protocol analysis.
Ab = antibody; ELISA = Enzyme-linked immunosorbent assay; gpELISA = Glycoprotein enzyme-linked immunosorbent assay; CI = Confidence interval.

Table 16: Statistical Analysis of Non-Inferiority in GMTs to S. pneumoniae Serotypes at 6 Weeks Postvaccination in the ProQuad + PCV7 [PCV7 = Pneumococcal 7-valent conjugate vaccine.] Treatment Group and the PCV7 Followed by ProQuad Control Group (Per-Protocol Analysis)
 |  | Group 1 ProQuad + PCV7 (N=510) |  | Group 2 PCV7 followed by ProQuad (N=258)
Serotype | Parameter | n | Estimated Response [Estimated responses and their fold-difference were based on statistical analysis models adjusting for study center and prevaccination titer.] | n | Estimated Response | Fold-Difference, [ProQuad + PCV7 / PCV7 followed by ProQuad. The conclusion of non-inferiority is based on the lower bound of the 2-sided 95% CI on the fold-difference being greater than 0.5, (i.e., excluding a decrease of 2-fold or more). This indicates that the fold-difference is statistically significantly less than the pre-specified clinically relevant 2-fold difference at the 1-sided alpha = 0.025 level.] (95% CI)
4 | GMT | 410 | 1.5 | 193 | 1.3 | 1.2 (1.0, 1.4)
6B | GMT | 410 | 8.9 | 192 | 8.4 | 1.1 (0.9, 1.2)
9V | GMT | 409 | 2.9 | 193 | 2.5 | 1.2 (1.0, 1.3)
14 | GMT | 408 | 6.5 | 193 | 5.7 | 1.1 (1.0, 1.3)
18C | GMT | 408 | 2.3 | 193 | 2.0 | 1.2 (1.0, 1.3)
19F | GMT | 408 | 3.5 | 192 | 3.1 | 1.1 (1.0, 1.3)
23F | GMT | 413 | 4.1 | 197 | 3.7 | 1.1 (1.0, 1.3)
N = Number of subjects vaccinated in each treatment group; n = Number of subjects contributing to the per-protocol analysis for the given serotype; GMT = geometric mean titer; CI = Confidence interval.

In a clinical trial, 653 healthy children 12 to 15 months of age were randomized to receive VAQTA, ProQuad subcutaneously, and pneumococcal 7-valent conjugate vaccine concomitantly (N=330) or ProQuad subcutaneously, and pneumococcal 7-valent conjugate vaccine concomitantly followed by VAQTA 6 weeks later (N=323) [see Adverse Reactions (6.1) for ethnicity and gender information]. Statistical analysis of non-inferiority of the response rate for varicella antibody at 6 weeks postvaccination among subjects who received VAQTA concomitantly or non-concomitantly with ProQuad and pneumococcal 7-valent conjugate vaccine is shown in Table 17. For the varicella component of ProQuad, in subjects with baseline antibody titers <1.25 gpELISA units/mL, the proportion with a titer ≥5 gpELISA units/mL 6 weeks after their first dose of ProQuad was non-inferior when ProQuad was administered with VAQTA and pneumococcal 7-valent conjugate vaccine as compared to the proportion with a titer ≥5 gpELISA units/mL when ProQuad was administered with pneumococcal 7-valent conjugate vaccine alone. Statistical analysis of non-inferiority of the seropositivity rate for hepatitis A antibody at 4 weeks postdose 2 of VAQTA among subjects who received VAQTA concomitantly or non-concomitantly with ProQuad and pneumococcal 7-valent conjugate vaccine is shown in Table 18. The seropositivity rate to hepatitis A 4 weeks after a second dose of VAQTA given concomitantly with ProQuad and pneumococcal 7-valent conjugate vaccine (defined as the percent of subjects with a titer ≥10 mIU/mL) was non-inferior to the seropositivity rate observed when VAQTA was administered separately from ProQuad and pneumococcal 7-valent conjugate vaccine. Statistical analysis of non-inferiority in GMT to S. pneumoniae serotypes at 6 weeks postvaccination among subjects who received VAQTA concomitantly or non-concomitantly with ProQuad and pneumococcal 7-valent conjugate vaccine is shown in Table 19. Additionally, the GMTs for S. pneumoniae types 4, 6B, 9V, 14, 18C, 19F, and 23F 6 weeks after vaccination with pneumococcal 7-valent conjugate vaccine administered concomitantly with ProQuad and VAQTA were non-inferior as compared to GMTs observed in the group given pneumococcal 7-valent conjugate vaccine with ProQuad alone. An earlier clinical study involving 617 healthy children provided data that indicated that the seroresponse rates 6 weeks post vaccination for measles, mumps, and rubella in those given M-M-R II and VAQTA concomitantly (N=309) were non-inferior as compared to historical controls.

Table 17: Statistical Analysis of Non-Inferiority of the Response Rate for Varicella Antibody at 6 Weeks Postvaccination Among Subjects Who Received VAQTA Concomitantly or Non-Concomitantly With ProQuad and PCV7 [PCV7 = Pneumococcal 7-valent conjugate vaccine.] (Per-Protocol Analysis Set)
 | Group 1: Concomitant VAQTA with ProQuad + PCV7 (N=330) |  | Group 2: Non-concomitant VAQTA separate from ProQuad + PCV7 (N=323) |  | Difference [Estimated responses and their differences were based on a statistical analysis model adjusting for combined study center.] (percentage points): Group 1 – Group 2 (95% CI)
Parameter | n | Estimated Response | n | Estimated Response | Difference [Estimated responses and their differences were based on a statistical analysis model adjusting for combined study center.] (percentage points): Group 1 – Group 2 (95% CI)
% ≥5 gpELISA units/mL [6 weeks following Dose 1.] | 225 [Initial Serostatus <1.25 gpELISA units/ mL. The conclusion of similarity (non-inferiority) was based on the lower bound of the 2-sided 95% CI on the risk difference excluding a decrease of 10 percentage points or more (lower bound >-10.0). This indicated that the risk difference was statistically significantly greater than the pre-specified clinically relevant difference of -10 percentage points at the 1-sided alpha = 0.025 level.] | 93.2% | 232 | 98.3% | -5.1 (-9.3, -1.4)
N = Number of subjects enrolled/randomized; n = Number of subjects contributing to the per-protocol analysis for varicella; CI = Confidence interval.

Table 18: Statistical Analysis of Non-Inferiority of the Seropositivity Rate (SPR) for Hepatitis A Antibody at 4 Weeks Postdose 2 of VAQTA Among Subjects Who Received VAQTA Concomitantly or Non-Concomitantly With ProQuad and PCV7 [PCV7 = Pneumococcal 7-valent conjugate vaccine.] (Per-Protocol Analysis Set)
 | Group 1: Concomitant VAQTA with ProQuad + PCV7 (N=330) |  | Group 2: Non-concomitant VAQTA separate from ProQuad + PCV7 (N=323) |  | Difference [Estimated responses and their differences were based on a statistical analysis model adjusting for combined study center.] (percentage points): Group 1 - Group 2 (95% CI)
Parameter | n | Estimated Response | n | Estimated Response | Difference [Estimated responses and their differences were based on a statistical analysis model adjusting for combined study center.] (percentage points): Group 1 - Group 2 (95% CI)
% ≥10 mIU/mL [4 weeks following receipt of 2 doses of VAQTA.] | 182 [Regardless of initial serostatus. The conclusion of non-inferiority was based on the lower bound of the 2-sided 95% CI on the risk difference being greater than -10 percentage points (i.e., excluding a decrease of 10 percentage points or more) (lower bound >-10.0). This indicated that the risk difference was statistically significantly greater than the pre-specified clinically relevant difference of -10 percentage points at the 1-sided alpha = 0.025 level.] | 100.0% | 159 | 99.3% | 0.7 (-1.4, 3.8)
CI = Confidence interval; N = Number of subjects enrolled/randomized; n = Number of subjects contributing to the per-protocol analysis for hepatitis A.

Table 19: Statistical Analysis of Non-Inferiority in Geometric Mean Titers (GMT) to S. pneumoniae Serotypes at 6 Weeks Postvaccination Among Subjects Who Received VAQTA Concomitantly or Non-Concomitantly With ProQuad and PCV7 [PCV7 = Pneumococcal 7-valent conjugate vaccine.] (Per-Protocol Analysis Set)
 | Group 1: Concomitant VAQTA with ProQuad + PCV7 (N=330) |  | Group 2: Non-concomitant VAQTA separate from ProQuad + PCV7 (N=323)
Serotype | n | Estimated Response [Estimated responses and their fold-difference were based on statistical analysis models adjusting for combined study center and prevaccination titer. The conclusion of non-inferiority was based on the lower bound of the 2-sided 95% CI on the fold-difference being greater than 0.5 (i.e., excluding a decrease of 2-fold or more). This indicates that the fold-difference was statistically significantly less than the prespecified clinically relevant 2-fold difference at the 1-sided alpha = 0.025 level.] | n | Estimated Response | Fold-Difference (95% CI)
4 | 246 | 1.9 | 247 | 1.7 | 1.1 (0.9, 1.3)
6B | 246 | 9.9 | 246 | 9.9 | 1.0 (0.8, 1.2)
9V | 247 | 3.7 | 247 | 4.2 | 0.9 (0.8, 1.0)
14 | 248 | 7.8 | 247 | 7.6 | 1.0 (0.9, 1.2)
18C | 247 | 2.9 | 247 | 2.7 | 1.1 (0.9, 1.3)
19F | 248 | 4.0 | 248 | 3.8 | 1.1 (0.9, 1.2)
23F | 247 | 5.1 | 247 | 4.4 | 1.1 (1.0, 1.3)
CI = Confidence interval; GMT = Geometric mean titer; N = Number of subjects enrolled/randomized; n = Number of subjects contributing to the per-protocol analysis for S. pneumoniae serotypes.

ProQuad Administered with Diphtheria and Tetanus Toxoids and Acellular Pertussis Vaccine Adsorbed (DTaP) and Haemophilus influenzae type b Conjugate (Meningococcal Protein Conjugate) and Hepatitis B (Recombinant) Vaccine

In a clinical trial, 1913 healthy children 12 to 15 months of age were randomized to receive ProQuad subcutaneously plus diphtheria and tetanus toxoids and acellular pertussis vaccine adsorbed (DTaP) and Haemophilus influenzae type b conjugate (meningococcal protein conjugate) and hepatitis B (recombinant) vaccine concomitantly at separate injection sites (N=949), ProQuad at the initial visit followed by DTaP and Haemophilus b conjugate and hepatitis B (recombinant) vaccine given concomitantly 6 weeks later (N=485), or M-M-R II and VARIVAX given concomitantly at separate injection sites (N=479) at the first visit [see Adverse Reactions (6.1) for ethnicity and gender information]. Seroconversion rates and antibody titers for measles, mumps, rubella, varicella, anti-PRP, and hepatitis B were comparable between the 2 groups given ProQuad at approximately 6 weeks postvaccination indicating that ProQuad and Haemophilus b conjugate (meningococcal protein conjugate) and hepatitis B (recombinant) vaccine may be administered concomitantly at separate injection sites (see Table 20 below). Response rates for measles, mumps, rubella, varicella, Haemophilus influenzae type b, and hepatitis B were not inferior in children given ProQuad plus Haemophilus influenzae type b conjugate (meningococcal protein conjugate) and hepatitis B (recombinant) vaccines concomitantly when compared to ProQuad at the initial visit and Haemophilus influenzae type b conjugate (meningococcal protein conjugate) and hepatitis B (recombinant) vaccines given concomitantly 6 weeks later. There are insufficient data to support concomitant vaccination with diphtheria and tetanus toxoids and acellular pertussis vaccine adsorbed (data not shown).

Table 20: Summary of the Comparison of the Immunogenicity Endpoints for Measles, Mumps, Rubella, Varicella, Haemophilus influenzae type b, and Hepatitis B Responses Following Vaccination with ProQuad, Haemophilus influenzae type b Conjugate (Meningococcal Protein Conjugate), and Hepatitis B (Recombinant) Vaccine and DTaP Administered Concomitantly Versus Non-Concomitant Vaccination with ProQuad Followed by These Vaccines
 |  | Concomitant Group | Non-Concomitant Group
 |  | N=949 | N=485
Vaccine Antigen | Parameter | Response | Response | Risk Difference (95% CI) | Criterion for Non-inferiority
Measles | % ≥120 mIU/mL | 97.8% | 98.7% | -0.9 (-2.3, 0.6) | LB >-5.0
Mumps | % ≥10 ELISA Ab units/mL | 95.4% | 95.1% | 0.3 (-1.7, 2.6) | LB >-5.0
Rubella | % ≥10 IU/mL | 98.6% | 99.3% | -0.7 (-1.8, 0.5) | LB >-5.0
Varicella | % ≥5 gpELISA units/mL | 89.6% | 90.8% | -1.2 (-4.1, 2.0) | LB >-10.0
HiB-PRP | % ≥1.0 mcg/mL | 94.6% | 96.5% | -1.9 (-4.1, 0.8) | LB >-10.0
HepB | % ≥10 mIU/mL | 95.9% | 98.8% | -2.8 (-4.8, -0.8) | LB >10.0
HiB-PRP = Haemophilus influenzae type b, polyribosyl phosphate; HepB = hepatitis B; LB = lower bound, limit for non-inferiority comparison.

15 REFERENCES

1. Kelso, J.M.; Jones, R.T.; Yunginger, J.W.: Anaphylaxis to measles, mumps, and rubella vaccine mediated by IgE to gelatin, J. Allergy Clin. Immunol. 91: 867-872, 1993.
2. Bitnum, A.; et al: Measles Inclusion Body Encephalitis Caused by the Vaccine Strain of Measles Virus. Clin. Infect. Dis. 29: 855-861, 1999. 5.
3. Angel, J.B.; et al: Vaccine Associated Measles Pneumonitis in an Adult with AIDS. Annals of Internal Medicine, 129: 104-106, 1998.
4. Levy O, et al. Disseminated varicella infection due to the vaccine strain of varicella-zoster virus, in a patient with a novel deficiency in natural killer T cells. J Infect Dis. 188(7):948-53, 2003.
5. Committee on Infectious Diseases, American Academy of Pediatrics. In: Pickering LK, Baker CJ, Overturf GD, et al., eds. Red Book: 2003 Report of the Committee on Infectious Diseases. 26th ed. Elk Grove Village, IL: American Academy of Pediatrics. 419-29, 2003.
6. Cecinati V, et al. Vaccine administration and the development of immune thrombocytopenic purpura in children. Human Vaccines & Immunotherapeutics 9:5, 2013.
7. Mantadakis E, Farmaki E, Buchanan GR. Thrombocytopenic Purpura after Measles-Mumps-Rubella Vaccination: A Systematic Review of the Literature and Guidance for Management J Ped 156 (4): 2010.
8. Andrews N, Stowe J, Miller E, Svanstrom H, Johansen K, Bonhoeffer J, et al. A collaborative approach to investigating the risk of thrombocytopenic purpura after measles-mumps-rubella vaccination in England and Denmark. Vaccine. 2012;30:3042-6.
9. Rubella Prevention: Recommendation of the Immunization Practices Advisory Committee (ACIP), MMWR 39(RR-15): 1-18, November 23, 1990.
10. Peter, G.; et al (eds): Report of the Committee on Infectious Diseases, Twenty-fourth Edition, American Academy of Pediatrics, 344-357, 1997.
11. Measles Prevention: Recommendations of the Immunization Practices Advisory Committee (ACIP), MMWR 38(S-9): 5-22, December 29, 1989.
12. Recommendations of the Immunization Practices Advisory Committee (ACIP), Mumps Prevention. MMWR. 38(22):388-392, 397-400, 1989.
13. Eberhart-Phillips, J.E.; et al: Measles in pregnancy: a descriptive study of 58 cases. Obstetrics and Gynecology, 82(5): 797-801, November 1993.
14. Jespersen, C.S.; et al: Measles as a cause of fetal defects: A retrospective study of ten measles epidemics in Greenland. Acta Paediatr Scand. 66: 367-372, May 1977.
15. Rynn L, Cragan J, Correa A. Update on overall prevalence of major birth defects Atlanta, 1978-2005. CDC MMWR. 57(01):1-5, January 11, 2008.
16. American College of Obstetricians and Gynecologists Frequently Asked Questions: Miscarriage and Molar Pregnancy, 2011.
17. Rubella vaccination during pregnancy--United States, 1971-1988. MMWR Morb Mortal Wkly Rep. 1989 May 5;38(17):289-93.
18. Bouthry, E.; Queinnec, C.; Vauzelle, C.; Vauloup-Fellous, C.: Congenital rubella syndrome following rubella vaccination during pregnancy. Pediatrics, 2023 Sep; 152 (3): e2022057627.
19. Yamauchi T, Wilson C, Geme JW Jr. Transmission of live, attenuated mumps virus to the human placenta. N Engl J Med. 1974;290(13):710‐712.
20. Bohlke K, Galil K, Jackson LA, et al. Postpartum varicella vaccination: Is the vaccine virus excreted in breast milk? Obstetrics and Gynecology. 102(5):970-977, 2003.
21. Dolbear GL, Moffat J, Falkner C and Wojtowycz M. A Pilot Study: Is attenuated varicella virus present in breast milk after postpartum immunization? Obstetrics and Gynecology. 101(4 Suppl.):47S-47S, 2003.
22. Weibel RE, et al. Clinical and laboratory studies of combined live measles, mumps, and rubella vaccines using the RA 27/3 rubella virus. Proc Soc Exp Biol Med. 165(2):323-326, 1980.
23. Watson, J.C.; Pearson, J.S.; Erdman, D.D.; et al: An Evaluation of Measles Revaccination Among School-Entry Age Children, 31st Interscience Conference on Antimicrobial Agents and Chemotherapy, Abstract #268, 143, 1991.
24. Unpublished data from the files of Research Laboratories of Merck Sharp & Dohme LLC, Rahway, NJ, USA.
25. Davidkin, I.; Jokinen, S.; Broman, M. et al.: Persistence of Measles, Mumps, and Rubella Antibodies in an MMR-Vaccinated Cohort: A 20-Year Follow-up, JID 197:950–6, April 2008.
26. LeBaron, W.; Beeler J.; Sullivan, B.; et al.: Persistence of Measles Antibodies After 2 Doses of Measles Vaccine in a Postelimination Environment, Arch Pediatr Adolesc Med. 161:294-301, March 2007.
27. LeBaron, C.; Forghani, B.; Beck, C. et al.: Persistence of Mumps Antibodies after 2 Doses of Measles-Mumps-Rubella Vaccine, JID 199:552– 60 , February 2009.
28. LeBaron, W.; Forghani, B.; Matter, L. et al.: Persistence of Rubella Antibodies after 2 Doses of Measles-Mumps-Rubella Vaccine, JID 200:888–99, September 2009.
29. Hilleman MR, Stokes J, Jr., Buynak EB, Weibel R, Halenda R, Goldner H. Studies of live attenuated measles virus vaccine in man: II. appraisal of efficacy. Am J Public Health. 52(2):44-56, 1962.
30. Krugman S, Giles JP, Jacobs AM. Studies on an attenuated measles-virus vaccine: VI. clinical, antigenic and prophylactic effects of vaccine in institutionalized children. N Engl J Med. 263(4):174-7, 1960.
31. Hilleman MR, Weibel RE, Buynak EB, Stokes J, Jr., Whitman JE, Jr. Live, attenuated mumps-virus vaccine. 4. Protective efficacy as measured in a field evaluation. N Engl J Med. 276(5):252-8, 1967.
32. Sugg WC, Finger JA, Levine RH, Pagano JS. Field evaluation of live virus mumps vaccine. J Pediatr. 72(4):461-6, 1968.
33. The Benevento and Compobasso Pediatricians Network for the Control of Vaccine-Preventable Diseases, D'Argenio P, Citarella A, Selvaggi MTM. Field evaluation of the clinical effectiveness of vaccines against pertussis, measles, rubella and mumps. Vaccine. 16(8):818-22, 1998.
34. Furukawa T, Miyata T, Kondo K, Kuno K, Isomura S, Takekoshi T. Rubella vaccination during an epidemic. JAMA. 213(6):987-90, 1970.
35. Vazquez M, et al. The effectiveness of the varicella vaccine in clinical practice. N Engl J Med. 344(13):955-960, 2001.
36. Kuter B, et al. Ten year follow-up of healthy children who received one or two injections of varicella vaccine. Pediatr Infect Dis J. 23(2):132-137, 2004.

16 HOW SUPPLIED/STORAGE AND HANDLING

ProQuad is supplied as follows:

(1) a package of 10 single-dose vials of lyophilized vaccine, NDC 0006-4171-00 (package A)

(2) a separate package of 10 prefilled syringes of sterile diluent, NDC 0006-4175-88 (package B) OR a separate package of 10 vials of sterile diluent, NDC 0006-4309-00 (package B)

Storage

Vaccine Vial

To maintain potency, ProQuad must be stored frozen between -58°F and +5°F (-50°C to -15°C). Use of dry ice may subject ProQuad to temperatures colder than -58°F (-50°C).

Before reconstitution, store the lyophilized vaccine in a freezer at a temperature between −58°F and +5°F (−50°C and −15°C) for up to 18 months. Any freezer (e.g., chest, frost-free) that reliably maintains an average temperature between −58°F and +5°F (−50°C and −15°C) and has a separate sealed freezer door is acceptable for storing ProQuad. Routine defrost cycling of a frost-free freezer is acceptable.

ProQuad may be stored at refrigerator temperature (36° to 46°F, 2° to 8°C) for up to 72 hours prior to reconstitution. Discard any ProQuad vaccine stored at 36° to 46°F which is not used within 72 hours of removal from 5°F (-15°C) storage.

Protect the vaccine from light at all times since such exposure may inactivate the vaccine viruses.

Sterile Diluent

The sterile diluent should be stored at room temperature (68° to 77°F, 20° to 25°C), or in a refrigerator (36° to 46°F, 2° to 8°C).

IF NOT USED IMMEDIATELY, THE RECONSTITUTED VACCINE MAY BE STORED AT ROOM TEMPERATURE, PROTECTED FROM LIGHT, FOR UP TO 30 MINUTES.

DISCARD RECONSTITUTED VACCINE IF IT IS NOT USED WITHIN 30 MINUTES.

DO NOT FREEZE RECONSTITUTED VACCINE.

For information regarding the product or questions regarding storage conditions, call 1-800-637-2590.

17 PATIENT COUNSELING INFORMATION

Advise the patient to read the FDA-approved patient labeling (Patient Information).

Instructions

Provide the required vaccine information to the patient, parent, or guardian.

Inform the patient, parent, or guardian of the benefits and risks associated with vaccination.

Inform the patient, parent, or guardian that the vaccine recipient should avoid use of salicylates for 6 weeks after vaccination with ProQuad [see Warnings and Precautions (5.8) and Drug Interactions (7.3)].

Question females of reproductive potential regarding the possibility of pregnancy prior to administration of ProQuad. Instruct these individuals to avoid pregnancy for 3 months following vaccination [see Contraindications (4.5) and Use in Specific Populations (8.1)].

Inform patients, parents, or guardians that vaccination with ProQuad may not offer 100% protection from measles, mumps, rubella, and varicella infection.

Instruct patients, parents, or guardians to report any adverse reactions to their health care provider. The U.S. Department of Health and Human Services has established a Vaccine Adverse Event Reporting System (VAERS) to accept all reports of suspected adverse events after the administration of any vaccine, including but not limited to the reporting of events required by the National Childhood Vaccine Injury Act of 1986. For information or a copy of the vaccine reporting form, call the VAERS toll-free number at 1-800-822-7967, or report online at www.vaers.hhs.gov .

Dist. by: Merck Sharp & Dohme LLC
Rahway, NJ 07065, USA

For patent information: www.msd.com/research/patent

Copyright © 2005-2025 Merck & Co., Inc., Rahway, NJ, USA, and its affiliates.
All rights reserved.

uspi-v221-i-fro-rha-2511r017

Patient Information
ProQuad® (pronounced “pro kwod”)
Measles, Mumps, Rubella, Varicella Virus Vaccine Live
Frozen Formulation

This is a summary of information about ProQuad®. You should read it before your child receives each dose of the vaccine. If you have any questions about the vaccine after reading this leaflet, you should ask your healthcare provider. This information does not take the place of talking about ProQuad with your healthcare provider.

What is ProQuad?

- ProQuad is a vaccine that helps prevent measles (rubeola), mumps, rubella (German measles), and chickenpox (varicella).
- It is for children 12 months to 12 years of age.
- ProQuad contains weakened live forms of measles virus, mumps virus, rubella virus, and chickenpox virus.
- ProQuad works by helping the immune system protect your child from getting measles, mumps, rubella, or chickenpox.
- ProQuad may not protect everyone who gets the vaccine.
- ProQuad does not treat measles, mumps, rubella, or chickenpox once your child has them.

What are measles, mumps, rubella, and chickenpox?

Measles is also known as rubeola. It is a serious illness. Measles virus can be passed to others if you have it. Measles can give you a high fever, cough, and a rash. The illness can last for 1 to 2 weeks. In rare cases, it can also cause an infection of the brain. This could lead to seizures, hearing loss, intellectual disability, and even death.

Mumps can also be passed to others. This virus can cause fever and headache. It can also make the glands under your jaw swell and be painful. The illness often lasts for several days. Sometimes, mumps can make the testicles swell and be painful. In some cases, it can cause meningitis, which is a swelling of the coverings of the brain and spinal cord.

Rubella is also known as German measles. It is often a mild illness. Rubella virus can cause a mild fever, swollen glands in the neck, pain and swelling in the joints, and a rash that lasts for a short time. It can be very dangerous if a pregnant woman catches it. Women who catch German measles when they are pregnant can have babies who are stillborn. Also, the babies may be blind or deaf, or have heart disease or intellectual disability.

Chickenpox is an illness that occurs most often in children who are 5 to 9 years old. It can be passed to others. The illness can include headache, fever, and general discomfort. Then an itchy rash occurs, which can turn into blisters. The most common complication is that the blisters can get infected. Less common but very serious complications can occur. These include pneumonia, inflammation of the brain, Reye syndrome (which affects the liver and the brain), and death. Severe disease and serious complications are more likely to occur in adolescents and adults.

Who should not get ProQuad?

Your child should not get ProQuad if he or she:

- is allergic to ProQuad or any of its ingredients. This includes gelatin or neomycin. (See the ingredient list at the end of this leaflet.)
- has a weakened immune system (which includes taking high doses of steroids by mouth or in a shot).
- has a fever.
- has active tuberculosis that is not treated.
- is pregnant or plans to get pregnant within the next 3 months.

What should I tell my child’s healthcare provider before my child gets ProQuad?

Tell your healthcare provider if your child:

- has or had any medical problems.
- has a history of seizures or someone in your family has a history of seizures.
- has received blood or plasma transfusions or human serum globulin.
- takes any medicines. (This includes non-prescription medicines and dietary supplements.)
- has any allergies. (This includes allergies to neomycin or gelatin.)
- had an allergic reaction to any other vaccine.
- has or had a low blood platelet count.
- is allergic to eggs.
- has a family member with a weakened immune system.

How is ProQuad given?

ProQuad is a shot given in the arm or thigh.

Your child will get 2 doses on two different dates:

- The first shot is given at 12 to 15 months old but may be given anytime through 12 years old.
- The second shot is given at 4 to 6 years old.

There should be at least 1 month between a dose of a measles-containing vaccine and a dose of ProQuad. There should be at least 3 months between a dose of a varicella-containing vaccine and a dose of ProQuad.

Your healthcare provider will decide the best time and number of shots by using official recommendations.

If a dose is missed, your healthcare provider will let you know when your child should get it.

What should my child avoid when getting ProQuad?

Do not take aspirin or aspirin-containing products for 6 weeks after getting ProQuad.

It is possible to catch chickenpox from a person who has been vaccinated with ProQuad. For 6 weeks after getting ProQuad, your child should avoid close contact with the following:

- people who are not vaccinated or who didn’t have chickenpox.
- people who have a weakened immune system.
- pregnant women who have never had chickenpox.
- newborn babies whose mothers have never had chickenpox.
- newborn babies born at less than 28 weeks of pregnancy.

What are the possible side effects of ProQuad?

The most common side effects reported after getting ProQuad are:

- pain, tenderness, soreness, redness, or swelling at the site of the shot
- fever
- irritability
- rash (including measles-like rash and chickenpox-like rash)

If your child has any of the following problems, tell your healthcare provider right away because these may be signs of an allergic reaction:

- trouble breathing
- wheezing
- hives
- rash

If your child has any side effects that worry you or seem to get worse, tell your healthcare provider right away.

These are not all the possible side effects of ProQuad. For more information, ask your healthcare provider. Contact your healthcare provider if your child has any new or unusual symptoms after receiving ProQuad.

Report the following to your healthcare provider.

- any side effects following vaccination
- exposure to ProQuad during pregnancy
- exposure to ProQuad during the 3 months before getting pregnant

You may also report any side effects directly to the Vaccine Adverse Event Reporting System (VAERS) at 1-800-822-7967 or www.vaers.hhs.gov , or to Merck Sharp and Dohme LLC at 1-877-888-4231.

What are the ingredients of ProQuad?

Active Ingredients: weakened forms of the measles, mumps, rubella, and varicella viruses.

Inactive Ingredients: sucrose, hydrolyzed gelatin, sodium chloride, sorbitol, monosodium L-glutamate, sodium phosphate dibasic, recombinant human albumin, sodium bicarbonate, potassium phosphate monobasic, potassium chloride, potassium phosphate dibasic, and residual components from the manufacturing process: MRC-5 cells including DNA and protein, neomycin, bovine calf serum, and other buffer and media ingredients.

ProQuad does not contain any preservatives.

What else should I know about ProQuad?

If you would like more information, talk to your healthcare provider or call 1-800-622-4477.

Dist. by: Merck Sharp & Dohme LLC
Rahway, NJ 07065, USA

For patent information: www.msd.com/research/patent

Copyright © 2005-2023 Merck & Co., Inc., Rahway, NJ, USA, and its affiliates.
All rights reserved.

usppi-v221-i-fro-rha-2303r001

This Patient Information has been approved by the U.S. Food and Drug Administration.

Revised: 03/2023

PRINCIPAL DISPLAY PANEL - 0.5 mL Vial Carton

NDC 0006-4171-00
10 Single-dose 0.5-mL Vials

A

Measles, Mumps, Rubella and Varicella
Virus Vaccine Live
ProQuad®

STORE FROZEN

Measles vaccine: More attenuated Enders' Edmonston strain. Chick cell tissue culture origin.
Mumps vaccine: Jeryl Lynn™ strain. Chick cell tissue culture origin.
Rubella vaccine: Wistar RA 27/3 strain. Human diploid cell (WI-38) culture origin.
Varicella vaccine: Oka/Merck strain. Human diploid cell (MRC-5) culture origin.

Contains no preservative. Contains trace quantities of neomycin.

Rx only